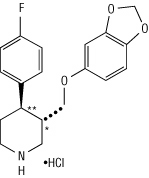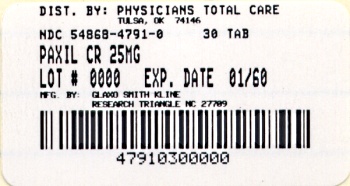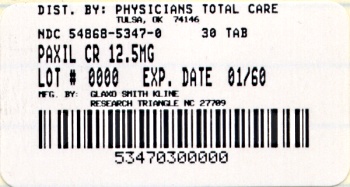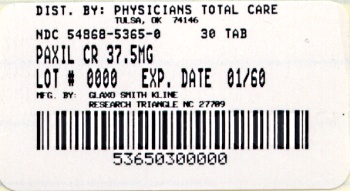 DRUG LABEL: PAXILCR
                      
NDC: 54868-5347 | Form: TABLET, FILM COATED, EXTENDED RELEASE
Manufacturer: Physicians Total Care, Inc.
Category: prescription | Type: HUMAN PRESCRIPTION DRUG LABEL
Date: 20110715

ACTIVE INGREDIENTS: PAROXETINE HYDROCHLORIDE 12.5 mg/1 1
INACTIVE INGREDIENTS: HYPROMELLOSES; POVIDONE K30; LACTOSE MONOHYDRATE; MAGNESIUM STEARATE; SILICON DIOXIDE; GLYCERYL BEHENATE; METHACRYLIC ACID - ETHYL ACRYLATE COPOLYMER (1:1) TYPE A; SODIUM LAURYL SULFATE; POLYSORBATE 80; TALC; TRIETHYL CITRATE; TITANIUM DIOXIDE

PAXIL CR®
(paroxetine hydrochloride)
Controlled-Release Tablets

Suicidality and Antidepressant Drugs

Antidepressants increased the risk compared to placebo of suicidal thinking and behavior (suicidality) in children, adolescents, and young adults in short-term studies of major depressive disorder (MDD) and other psychiatric disorders. Anyone considering the use of PAXIL CR or any other antidepressant in a child, adolescent, or young adult must balance this risk with the clinical need. Short-term studies did not show an increase in the risk of suicidality with antidepressants compared to placebo in adults beyond age 24; there was a reduction in risk with antidepressants compared to placebo in adults aged 65 and older. Depression and certain other psychiatric disorders are themselves associated with increases in the risk of suicide. Patients of all ages who are started on antidepressant therapy should be monitored appropriately and observed closely for clinical worsening, suicidality, or unusual changes in behavior. Families and caregivers should be advised of the need for close observation and communication with the prescriber. PAXIL CR is not approved for use in pediatric patients. (See WARNINGS: Clinical Worsening and Suicide Risk, PRECAUTIONS: Information for Patients, and PRECAUTIONS: Pediatric Use.)

DESCRIPTION

PAXIL CR (paroxetine hydrochloride) is an orally administered psychotropic drug with a chemical structure unrelated to other selective serotonin reuptake inhibitors or to tricyclic, tetracyclic, or other available antidepressant or antipanic agents. It is the hydrochloride salt of a phenylpiperidine compound identified chemically as (-)-trans-4R-(4'-fluorophenyl)-3S-[(3',4'-methylenedioxyphenoxy) methyl] piperidine hydrochloride hemihydrate and has the empirical formula of C19H20FNO3•HCl•1/2H2O. The molecular weight is 374.8 (329.4 as free base). The structural formula of paroxetine hydrochloride is:

Paroxetine hydrochloride is an odorless, off-white powder, having a melting point range of 120° to 138°C and a solubility of 5.4 mg/mL in water.

Each enteric, film-coated, controlled-release tablet contains paroxetine hydrochloride equivalent to paroxetine as follows: 12.5 mg–yellow, 25 mg–pink, 37.5 mg–blue. One layer of the tablet consists of a degradable barrier layer and the other contains the active material in a hydrophilic matrix.

Inactive ingredients consist of hypromellose, polyvinylpyrrolidone, lactose monohydrate, magnesium stearate, silicon dioxide, glyceryl behenate, methacrylic acid copolymer type C, sodium lauryl sulfate, polysorbate 80, talc, triethyl citrate, titanium dioxide, polyethylene glycols, and 1 or more of the following colorants: Yellow ferric oxide, red ferric oxide, D&C Red No. 30 aluminum lake, FD&C Yellow No. 6 aluminum lake, D&C Yellow No. 10 aluminum lake, FD&C Blue No. 2 aluminum lake.

CLINICAL PHARMACOLOGY

Pharmacodynamics

The efficacy of paroxetine in the treatment of major depressive disorder, panic disorder, social anxiety disorder, and premenstrual dysphoric disorder (PMDD) is presumed to be linked to potentiation of serotonergic activity in the central nervous system resulting from inhibition of neuronal reuptake of serotonin (5-hydroxy-tryptamine, 5-HT). Studies at clinically relevant doses in humans have demonstrated that paroxetine blocks the uptake of serotonin into human platelets. In vitro studies in animals also suggest that paroxetine is a potent and highly selective inhibitor of neuronal serotonin reuptake and has only very weak effects on norepinephrine and dopamine neuronal reuptake. In vitro radioligand binding studies indicate that paroxetine has little affinity for muscarinic, alpha1-, alpha2-, beta-adrenergic-, dopamine (D2)-, 5-HT1-, 5-HT2-, and histamine (H1)-receptors; antagonism of muscarinic, histaminergic, and alpha1-adrenergic receptors has been associated with various anticholinergic, sedative, and cardiovascular effects for other psychotropic drugs.

Because the relative potencies of paroxetine’s major metabolites are at most 1/50 of the parent compound, they are essentially inactive.

Pharmacokinetics

Paroxetine hydrochloride is completely absorbed after oral dosing of a solution of the hydrochloride salt. The elimination half-life is approximately 15 to 20 hours after a single dose of PAXIL CR. Paroxetine is extensively metabolized and the metabolites are considered to be inactive. Nonlinearity in pharmacokinetics is observed with increasing doses. Paroxetine metabolism is mediated in part by CYP2D6, and the metabolites are primarily excreted in the urine and to some extent in the feces. Pharmacokinetic behavior of paroxetine has not been evaluated in subjects who are deficient in CYP2D6 (poor metabolizers).

Absorption and Distribution

Tablets of PAXIL CR contain a degradable polymeric matrix (GEOMATRIX™) designed to control the dissolution rate of paroxetine over a period of approximately 4 to 5 hours. In addition to controlling the rate of drug release in vivo, an enteric coat delays the start of drug release until tablets of PAXIL CR have left the stomach.

Paroxetine hydrochloride is completely absorbed after oral dosing of a solution of the hydrochloride salt. In a study in which normal male and female subjects (n = 23) received single oral doses of PAXIL CR at 4 dosage strengths (12.5 mg, 25 mg, 37.5 mg, and 50 mg), paroxetine Cmax and AUC0-inf increased disproportionately with dose (as seen also with immediate-release formulations). Mean Cmax and AUC0-inf values at these doses were 2.0, 5.5, 9.0, and 12.5 ng/mL, and 121, 261, 338, and 540 ng•hr./mL, respectively. Tmax was observed typically between 6 and 10 hours post-dose, reflecting a reduction in absorption rate compared with immediate-release formulations. The bioavailability of 25 mg PAXIL CR is not affected by food.

Paroxetine distributes throughout the body, including the CNS, with only 1% remaining in the plasma.

Approximately 95% and 93% of paroxetine is bound to plasma protein at 100 ng/mL and 400 ng/mL, respectively. Under clinical conditions, paroxetine concentrations would normally be less than 400 ng/mL. Paroxetine does not alter the in vitro protein binding of phenytoin or warfarin.

Metabolism and Excretion

The mean elimination half-life of paroxetine was 15 to 20 hours throughout a range of single doses of PAXIL CR (12.5 mg, 25 mg, 37.5 mg, and 50 mg). During repeated administration of PAXIL CR (25 mg once daily), steady state was reached within 2 weeks (i.e., comparable to immediate-release formulations). In a repeat-dose study in which normal male and female subjects (n = 23) received PAXIL CR (25 mg daily), mean steady state Cmax, Cmin, and AUC0-24 values were 30 ng/mL, 20 ng/mL, and 550 ng•hr./mL, respectively.

Based on studies using immediate-release formulations, steady-state drug exposure based on AUC0-24 was several-fold greater than would have been predicted from single-dose data. The excess accumulation is a consequence of the fact that 1 of the enzymes that metabolizes paroxetine is readily saturable.

In steady-state dose proportionality studies involving elderly and nonelderly patients, at doses of the immediate-release formulation of 20 mg to 40 mg daily for the elderly and 20 mg to 50 mg daily for the nonelderly, some nonlinearity was observed in both populations, again reflecting a saturable metabolic pathway. In comparison to Cmin values after 20 mg daily, values after 40 mg daily were only about 2 to 3 times greater than doubled.

Paroxetine is extensively metabolized after oral administration. The principal metabolites are polar and conjugated products of oxidation and methylation, which are readily cleared. Conjugates with glucuronic acid and sulfate predominate, and major metabolites have been isolated and identified. Data indicate that the metabolites have no more than 1/50 the potency of the parent compound at inhibiting serotonin uptake. The metabolism of paroxetine is accomplished in part by CYP2D6. Saturation of this enzyme at clinical doses appears to account for the nonlinearity of paroxetine kinetics with increasing dose and increasing duration of treatment. The role of this enzyme in paroxetine metabolism also suggests potential drug-drug interactions (see PRECAUTIONS: Drugs Metabolized by CYP2D6).

Approximately 64% of a 30-mg oral solution dose of paroxetine was excreted in the urine with 2% as the parent compound and 62% as metabolites over a 10-day post-dosing period. About 36% was excreted in the feces (probably via the bile), mostly as metabolites and less than 1% as the parent compound over the 10-day post-dosing period.

Other Clinical Pharmacology Information

Specific Populations

Renal and Liver Disease

Increased plasma concentrations of paroxetine occur in subjects with renal and hepatic impairment. The mean plasma concentrations in patients with creatinine clearance below 30 mL/min. were approximately 4 times greater than seen in normal volunteers. Patients with creatinine clearance of 30 to 60 mL/min. and patients with hepatic functional impairment had about a 2-fold increase in plasma concentrations (AUC, Cmax).

The initial dosage should therefore be reduced in patients with severe renal or hepatic impairment, and upward titration, if necessary, should be at increased intervals (see DOSAGE AND ADMINISTRATION).

Elderly Patients

In a multiple-dose study in the elderly at daily doses of 20, 30, and 40 mg of the immediate-release formulation, Cmin concentrations were about 70% to 80% greater than the respective Cmin concentrations in nonelderly subjects. Therefore the initial dosage in the elderly should be reduced (see DOSAGE AND ADMINISTRATION).

Drug-Drug Interactions

In vitro drug interaction studies reveal that paroxetine inhibits CYP2D6. Clinical drug interaction studies have been performed with substrates of CYP2D6 and show that paroxetine can inhibit the metabolism of drugs metabolized by CYP2D6 including desipramine, risperidone, and atomoxetine (see PRECAUTIONS: Drug Interactions).

Major Depressive Disorder

The efficacy of PAXIL CR controlled-release tablets as a treatment for major depressive disorder has been established in two 12-week, flexible-dose, placebo-controlled studies of patients with DSM-IV Major Depressive Disorder. One study included patients in the age range 18 to 65 years, and a second study included elderly patients, ranging in age from 60 to 88. In both studies, PAXIL CR was shown to be significantly more effective than placebo in treating major depressive disorder as measured by the following: Hamilton Depression Rating Scale (HDRS), the Hamilton depressed mood item, and the Clinical Global Impression (CGI)–Severity of Illness score.

A study of outpatients with major depressive disorder who had responded to immediate-release paroxetine tablets (HDRS total score <8) during an initial 8-week open-treatment phase and were then randomized to continuation on immediate-release paroxetine tablets or placebo for 1 year demonstrated a significantly lower relapse rate for patients taking immediate-release paroxetine tablets (15%) compared to those on placebo (39%). Effectiveness was similar for male and female patients.

Panic Disorder

The effectiveness of PAXIL CR in the treatment of panic disorder was evaluated in three 10-week, multicenter, flexible-dose studies (Studies 1, 2, and 3) comparing paroxetine controlled-release (12.5 to 75 mg daily) to placebo in adult outpatients who had panic disorder (DSM-IV), with or without agoraphobia. These trials were assessed on the basis of their outcomes on 3 variables: (1) the proportions of patients free of full panic attacks at endpoint; (2) change from baseline to endpoint in the median number of full panic attacks; and (3) change from baseline to endpoint in the median Clinical Global Impression Severity score. For Studies 1 and 2, PAXIL CR was consistently superior to placebo on 2 of these 3 variables. Study 3 failed to consistently demonstrate a significant difference between PAXIL CR and placebo on any of these variables.

For all 3 studies, the mean dose of PAXIL CR for completers at endpoint was approximately 50 mg/day. Subgroup analyses did not indicate that there were any differences in treatment outcomes as a function of age or gender.

Long-term maintenance effects of the immediate-release formulation of paroxetine in panic disorder were demonstrated in an extension study. Patients who were responders during a 10-week double-blind phase with immediate-release paroxetine and during a 3-month double-blind extension phase were randomized to either immediate-release paroxetine or placebo in a 3-month double-blind relapse prevention phase. Patients randomized to paroxetine were significantly less likely to relapse than comparably treated patients who were randomized to placebo.

Social Anxiety Disorder

The efficacy of PAXIL CR as a treatment for social anxiety disorder has been established, in part, on the basis of extrapolation from the established effectiveness of the immediate-release formulation of paroxetine. In addition, the effectiveness of PAXIL CR in the treatment of social anxiety disorder was demonstrated in a 12-week, multicenter, double-blind, flexible-dose, placebo-controlled study of adult outpatients with a primary diagnosis of social anxiety disorder (DSM-IV). In the study, the effectiveness of PAXIL CR (12.5 to 37.5 mg daily) compared to placebo was evaluated on the basis of (1) change from baseline in the Liebowitz Social Anxiety Scale (LSAS) total score and (2) the proportion of responders who scored 1 or 2 (very much improved or much improved) on the Clinical Global Impression (CGI) Global Improvement score.

PAXIL CR demonstrated statistically significant superiority over placebo on both the LSAS total score and the CGI Improvement responder criterion. For patients who completed the trial, 64% of patients treated with PAXIL CR compared to 34.7% of patients treated with placebo were CGI Improvement responders.

Subgroup analyses did not indicate that there were any differences in treatment outcomes as a function of gender. Subgroup analyses of studies utilizing the immediate-release formulation of paroxetine generally did not indicate differences in treatment outcomes as a function of age, race, or gender.

Premenstrual Dysphoric Disorder

The effectiveness of PAXIL CR for the treatment of PMDD utilizing a continuous dosing regimen has been established in 2 placebo-controlled trials. Patients in these trials met DSM-IV criteria for PMDD. In a pool of 1,030 patients, treated with daily doses of PAXIL CR 12.5 or 25 mg/day, or placebo the mean duration of the PMDD symptoms was approximately 11 ± 7 years. Patients on systemic hormonal contraceptives were excluded from these trials. Therefore, the efficacy of PAXIL CR in combination with systemic (including oral) hormonal contraceptives for the continuous daily treatment of PMDD is unknown. In both positive studies, patients (N = 672) were treated with 12.5 mg/day or 25 mg/day of PAXIL CR or placebo continuously throughout the menstrual cycle for a period of 3 menstrual cycles. The VAS-Total score is a patient-rated instrument that mirrors the diagnostic criteria of PMDD as identified in the DSM-IV, and includes assessments for mood, physical symptoms, and other symptoms. 12.5 mg/day and 25 mg/day of PAXIL CR were significantly more effective than placebo as measured by change from baseline to the endpoint on the luteal phase VAS-Total score.

In a third study employing intermittent dosing, patients (N = 366) were treated for the 2 weeks prior to the onset of menses (luteal phase dosing, also known as intermittent dosing) with 12.5 mg/day or 25 mg/day of PAXIL CR or placebo for a period of 3 months. 12.5 mg/day and 25 mg/day of PAXIL CR, as luteal phase dosing, was significantly more effective than placebo as measured by change from baseline luteal phase VAS total score.

There is insufficient information to determine the effect of race or age on outcome in these studies.

INDICATIONS AND USAGE

Major Depressive Disorder

PAXIL CR is indicated for the treatment of major depressive disorder.

The efficacy of PAXIL CR in the treatment of a major depressive episode was established in two 12-week controlled trials of outpatients whose diagnoses corresponded to the DSM-IV category of major depressive disorder (see CLINICAL PHARMACOLOGY: Clinical Trials).

A major depressive episode (DSM-IV) implies a prominent and relatively persistent (nearly every day for at least 2 weeks) depressed mood or loss of interest or pleasure in nearly all activities, representing a change from previous functioning, and includes the presence of at least 5 of the following 9 symptoms during the same 2-week period: Depressed mood, markedly diminished interest or pleasure in usual activities, significant change in weight and/or appetite, insomnia or hypersomnia, psychomotor agitation or retardation, increased fatigue, feelings of guilt or worthlessness, slowed thinking or impaired concentration, a suicide attempt, or suicidal ideation.

The antidepressant action of paroxetine in hospitalized depressed patients has not been adequately studied.

PAXIL CR has not been systematically evaluated beyond 12 weeks in controlled clinical trials; however, the effectiveness of immediate-release paroxetine hydrochloride in maintaining a response in major depressive disorder for up to 1 year has been demonstrated in a placebo-controlled trial (see CLINICAL PHARMACOLOGY: Clinical Trials). The physician who elects to use PAXIL CR for extended periods should periodically re-evaluate the long-term usefulness of the drug for the individual patient (see DOSAGE AND ADMINISTRATION).

Panic Disorder

PAXIL CR is indicated for the treatment of panic disorder, with or without agoraphobia, as defined in DSM-IV. Panic disorder is characterized by the occurrence of unexpected panic attacks and associated concern about having additional attacks, worry about the implications or consequences of the attacks, and/or a significant change in behavior related to the attacks.

The efficacy of PAXIL CR controlled-release tablets was established in two 10-week trials in panic disorder patients whose diagnoses corresponded to the DSM-IV category of panic disorder (see CLINICAL PHARMACOLOGY: Clinical Trials).

Panic disorder (DSM-IV) is characterized by recurrent unexpected panic attacks, i.e., a discrete period of intense fear or discomfort in which 4 (or more) of the following symptoms develop abruptly and reach a peak within 10 minutes: (1) palpitations, pounding heart, or accelerated heart rate; (2) sweating; (3) trembling or shaking; (4) sensations of shortness of breath or smothering; (5) feeling of choking; (6) chest pain or discomfort; (7) nausea or abdominal distress; (8) feeling dizzy, unsteady, lightheaded, or faint; (9) derealization (feelings of unreality) or depersonalization (being detached from oneself); (10) fear of losing control; (11) fear of dying; (12) paresthesias (numbness or tingling sensations); (13) chills or hot flushes.

Long-term maintenance of efficacy with the immediate-release formulation of paroxetine was demonstrated in a 3-month relapse prevention trial. In this trial, patients with panic disorder assigned to immediate-release paroxetine demonstrated a lower relapse rate compared to patients on placebo (see CLINICAL PHARMACOLOGY: Clinical Trials). Nevertheless, the physician who prescribes PAXIL CR for extended periods should periodically re-evaluate the long-term usefulness of the drug for the individual patient (see DOSAGE AND ADMINISTRATION).

Social Anxiety Disorder

PAXIL CR is indicated for the treatment of social anxiety disorder, also known as social phobia, as defined in DSM-IV (300.23). Social anxiety disorder is characterized by a marked and persistent fear of 1 or more social or performance situations in which the person is exposed to unfamiliar people or to possible scrutiny by others. Exposure to the feared situation almost invariably provokes anxiety, which may approach the intensity of a panic attack. The feared situations are avoided or endured with intense anxiety or distress. The avoidance, anxious anticipation, or distress in the feared situation(s) interferes significantly with the person's normal routine, occupational or academic functioning, or social activities or relationships, or there is marked distress about having the phobias. Lesser degrees of performance anxiety or shyness generally do not require psychopharmacological treatment.

The efficacy of PAXIL CR as a treatment for social anxiety disorder has been established, in part, on the basis of extrapolation from the established effectiveness of the immediate-release formulation of paroxetine. In addition, the efficacy of PAXIL CR was established in a 12-week trial, in adult outpatients with social anxiety disorder (DSM-IV). PAXIL CR has not been studied in children or adolescents with social phobia (see CLINICAL PHARMACOLOGY: Clinical Trials).

The effectiveness of PAXIL CR in long-term treatment of social anxiety disorder, i.e., for more than 12 weeks, has not been systematically evaluated in adequate and well-controlled trials. Therefore, the physician who elects to prescribe PAXIL CR for extended periods should periodically re-evaluate the long-term usefulness of the drug for the individual patient (see DOSAGE AND ADMINISTRATION).

Premenstrual Dysphoric Disorder

PAXIL CR is indicated for the treatment of PMDD.

The efficacy of PAXIL CR in the treatment of PMDD has been established in 3 placebo-controlled trials (see CLINICAL PHARMACOLOGY: Clinical Trials).

The essential features of PMDD, according to DSM-IV, include markedly depressed mood, anxiety or tension, affective lability, and persistent anger or irritability. Other features include decreased interest in usual activities, difficulty concentrating, lack of energy, change in appetite or sleep, and feeling out of control. Physical symptoms associated with PMDD include breast tenderness, headache, joint and muscle pain, bloating, and weight gain. These symptoms occur regularly during the luteal phase and remit within a few days following the onset of menses; the disturbance markedly interferes with work or school or with usual social activities and relationships with others. In making the diagnosis, care should be taken to rule out other cyclical mood disorders that may be exacerbated by treatment with an antidepressant.

The effectiveness of PAXIL CR in long-term use, that is, for more than 3 menstrual cycles, has not been systematically evaluated in controlled trials. Therefore, the physician who elects to use PAXIL CR for extended periods should periodically re-evaluate the long-term usefulness of the drug for the individual patient (see DOSAGE AND ADMINISTRATION).

CONTRAINDICATIONS

The use of MAOIs intended to treat depression with, or within 14 days of treatment with, PAXIL CR is contraindicated (see WARNINGS).

Do not start PAXIL CR in a patient who is being treated with a reversible MAOI such as linezolid or methylene blue because of an increased risk of serotonin syndrome or neuroleptic malignant syndrome (NMS)-like reactions (see WARNINGS).

Concomitant use with thioridazine is contraindicated (see WARNINGS and PRECAUTIONS).

Concomitant use in patients taking pimozide is contraindicated (see PRECAUTIONS).

PAXIL CR is contraindicated in patients with a hypersensitivity to paroxetine or to any of the inactive ingredients in PAXIL CR.

WARNINGS

Clinical Worsening and Suicide Risk

Patients with major depressive disorder (MDD), both adult and pediatric, may experience worsening of their depression and/or the emergence of suicidal ideation and behavior (suicidality) or unusual changes in behavior, whether or not they are taking antidepressant medications, and this risk may persist until significant remission occurs. Suicide is a known risk of depression and certain other psychiatric disorders, and these disorders themselves are the strongest predictors of suicide. There has been a long-standing concern, however, that antidepressants may have a role in inducing worsening of depression and the emergence of suicidality in certain patients during the early phases of treatment. Pooled analyses of short-term placebo-controlled trials of antidepressant drugs (SSRIs and others) showed that these drugs increase the risk of suicidal thinking and behavior (suicidality) in children, adolescents, and young adults (ages 18-24) with major depressive disorder (MDD) and other psychiatric disorders. Short-term studies did not show an increase in the risk of suicidality with antidepressants compared to placebo in adults beyond age 24; there was a reduction with antidepressants compared to placebo in adults aged 65 and older.

The pooled analyses of placebo-controlled trials in children and adolescents with MDD, obsessive compulsive disorder (OCD), or other psychiatric disorders included a total of 24 short-term trials of 9 antidepressant drugs in over 4,400 patients. The pooled analyses of placebo-controlled trials in adults with MDD or other psychiatric disorders included a total of 295 short-term trials (median duration of 2 months) of 11 antidepressant drugs in over 77,000 patients. There was considerable variation in risk of suicidality among drugs, but a tendency toward an increase in the younger patients for almost all drugs studied. There were differences in absolute risk of suicidality across the different indications, with the highest incidence in MDD. The risk differences (drug vs placebo), however, were relatively stable within age strata and across indications. These risk differences (drug-placebo difference in the number of cases of suicidality per 1,000 patients treated) are provided in Table 1.

Table 1
Age Range | Drug-Placebo Difference in Number of Cases of Suicidality per 1,000 Patients Treated
Increases Compared to Placebo
<18 | 14 additional cases
18-24 | 5 additional cases
Decreases Compared to Placebo
25-64 | 1 fewer case
≥65 | 6 fewer cases

No suicides occurred in any of the pediatric trials. There were suicides in the adult trials, but the number was not sufficient to reach any conclusion about drug effect on suicide.

It is unknown whether the suicidality risk extends to longer-term use, i.e., beyond several months. However, there is substantial evidence from placebo-controlled maintenance trials in adults with depression that the use of antidepressants can delay the recurrence of depression.

All patients being treated with antidepressants for any indication should be monitored appropriately and observed closely for clinical worsening, suicidality, and unusual changes in behavior, especially during the initial few months of a course of drug therapy, or at times of dose changes, either increases or decreases.

The following symptoms, anxiety, agitation, panic attacks, insomnia, irritability, hostility, aggressiveness, impulsivity, akathisia (psychomotor restlessness), hypomania, and mania, have been reported in adult and pediatric patients being treated with antidepressants for major depressive disorder as well as for other indications, both psychiatric and nonpsychiatric. Although a causal link between the emergence of such symptoms and either the worsening of depression and/or the emergence of suicidal impulses has not been established, there is concern that such symptoms may represent precursors to emerging suicidality.

Consideration should be given to changing the therapeutic regimen, including possibly discontinuing the medication, in patients whose depression is persistently worse, or who are experiencing emergent suicidality or symptoms that might be precursors to worsening depression or suicidality, especially if these symptoms are severe, abrupt in onset, or were not part of the patient’s presenting symptoms.

If the decision has been made to discontinue treatment, medication should be tapered, as rapidly as is feasible, but with recognition that abrupt discontinuation can be associated with certain symptoms (see PRECAUTIONS and DOSAGE AND ADMINISTRATION: Discontinuation of Treatment With PAXIL CR, for a description of the risks of discontinuation of PAXIL CR).

Families and caregivers of patients being treated with antidepressants for major depressive disorder or other indications, both psychiatric and nonpsychiatric, should be alerted about the need to monitor patients for the emergence of agitation, irritability, unusual changes in behavior, and the other symptoms described above, as well as the emergence of suicidality, and to report such symptoms immediately to healthcare providers. Such monitoring should include daily observation by families and caregivers. Prescriptions for PAXIL CR should be written for the smallest quantity of tablets consistent with good patient management, in order to reduce the risk of overdose.

Screening Patients for Bipolar Disorder

A major depressive episode may be the initial presentation of bipolar disorder. It is generally believed (though not established in controlled trials) that treating such an episode with an antidepressant alone may increase the likelihood of precipitation of a mixed/manic episode in patients at risk for bipolar disorder. Whether any of the symptoms described above represent such a conversion is unknown. However, prior to initiating treatment with an antidepressant, patients with depressive symptoms should be adequately screened to determine if they are at risk for bipolar disorder; such screening should include a detailed psychiatric history, including a family history of suicide, bipolar disorder, and depression. It should be noted that PAXIL CR is not approved for use in treating bipolar depression.

Potential for Interaction With Monoamine Oxidase Inhibitors

In patients receiving another serotonin reuptake inhibitor drug in combination with monoamine oxidase inhibitors (MAOIs), including reversible MAOIs such as linezolid and methylene blue, there have been reports of serious, sometimes fatal, reactions including hyperthermia, rigidity, myoclonus, autonomic instability with possible rapid fluctuations of vital signs, and mental status changes that include extreme agitation progressing to delirium and coma. These reactions have also been reported in patients who have recently discontinued that drug and have been started on an MAOI. Some cases presented with features resembling serotonin syndrome or NMS-like reactions (see CONTRAINDICATIONS and DOSAGE AND ADMINISTRATION).

Serotonin Syndrome or Neuroleptic Malignant Syndrome (NMS)-like Reactions

The development of a potentially life-threatening serotonin syndrome or Neuroleptic Malignant Syndrome (NMS)-like reactions have been reported with SNRIs and SSRIs alone, including treatment with PAXIL CR, but particularly with concomitant use of serotonergic drugs (including triptans) with drugs which impair metabolism of serotonin (including MAOIs), or with antipsychotics or other dopamine antagonists. Serotonin syndrome symptoms may include mental status changes (e.g., agitation, hallucinations, coma), autonomic instability (e.g., tachycardia, labile blood pressure, hyperthermia), neuromuscular aberrations (e.g., hyperreflexia, incoordination) and/or gastrointestinal symptoms (e.g., nausea, vomiting, diarrhea). Serotonin syndrome, in its most severe form can resemble neuroleptic malignant syndrome, which includes hyperthermia, muscle rigidity, autonomic instability with possible rapid fluctuation of vital signs, and mental status changes. Patients should be monitored for the emergence of serotonin syndrome or NMS-like signs and symptoms.

The concomitant use of PAXIL CR with MAOIs intended to treat depression is contraindicated.

If concomitant treatment of PAXIL CR with a 5-hydroxytryptamine receptor agonist (triptan) is clinically warranted, careful observation of the patient is advised, particularly during treatment initiation and dose increases.

The concomitant use of PAXIL CR with serotonin precursors (such as tryptophan) is not recommended.

Treatment with PAXIL CR and any concomitant serotonergic or antidopaminergic agents, including antipsychotics, should be discontinued immediately if the above events occur and supportive symptomatic treatment should be initiated.

Potential Interaction With Thioridazine

Thioridazine administration alone produces prolongation of the QTc interval, which is associated with serious ventricular arrhythmias, such as torsade de pointes–type arrhythmias, and sudden death. This effect appears to be dose related.

An in vivo study suggests that drugs which inhibit CYP2D6, such as paroxetine, will elevate plasma levels of thioridazine. Therefore, it is recommended that paroxetine not be used in combination with thioridazine (see CONTRAINDICATIONS and PRECAUTIONS).

Usage in Pregnancy

Teratogenic Effects

Epidemiological studies have shown that infants exposed to paroxetine in the first trimester of pregnancy have an increased risk of congenital malformations, particularly cardiovascular malformations. The findings from these studies are summarized below:

- A study based on Swedish national registry data demonstrated that infants exposed to paroxetine during pregnancy (n = 815) had an increased risk of cardiovascular malformations (2% risk in paroxetine-exposed infants) compared to the entire registry population (1% risk), for an odds ratio (OR) of 1.8 (95% confidence interval 1.1 to 2.8). No increase in the risk of overall congenital malformations was seen in the paroxetine-exposed infants. The cardiac malformations in the paroxetine-exposed infants were primarily ventricular septal defects (VSDs) and atrial septal defects (ASDs). Septal defects range in severity from those that resolve spontaneously to those which require surgery.

- A separate retrospective cohort study from the United States (United Healthcare data) evaluated 5,956 infants of mothers dispensed antidepressants during the first trimester (n = 815 for paroxetine). This study showed a trend towards an increased risk for cardiovascular malformations for paroxetine (risk of 1.5%) compared to other antidepressants (risk of 1%), for an OR of 1.5 (95% confidence interval 0.8 to 2.9). Of the 12 paroxetine-exposed infants with cardiovascular malformations, 9 had VSDs. This study also suggested an increased risk of overall major congenital malformations including cardiovascular defects for paroxetine (4% risk) compared to other (2% risk) antidepressants (OR 1.8; 95% confidence interval 1.2 to 2.8).
- Two large case-control studies using separate databases, each with >9,000 birth defect cases and >4,000 controls, found that maternal use of paroxetine during the first trimester of pregnancy was associated with a 2- to 3-fold increased risk of right ventricular outflow tract obstructions. In one study the OR was 2.5 (95% confidence interval, 1.0 to 6.0, 7 exposed infants) and in the other study the OR was 3.3 (95% confidence interval, 1.3 to 8.8, 6 exposed infants).

Other studies have found varying results as to whether there was an increased risk of overall, cardiovascular, or specific congenital malformations. A meta-analysis of epidemiological data over a 16-year period (1992 to 2008) on first trimester paroxetine use in pregnancy and congenital malformations included the above-noted studies in addition to others (n = 17 studies that included overall malformations and n = 14 studies that included cardiovascular malformations; n = 20 distinct studies). While subject to limitations, this meta-analysis suggested an increased occurrence of cardiovascular malformations (prevalence odds ratio [POR] 1.5; 95% confidence interval 1.2 to 1.9) and overall malformations (POR 1.2; 95% confidence interval 1.1 to 1.4) with paroxetine use during the first trimester. It was not possible in this meta-analysis to determine the extent to which the observed prevalence of cardiovascular malformations might have contributed to that of overall malformations, nor was it possible to determine whether any specific types of cardiovascular malformations might have contributed to the observed prevalence of all cardiovascular malformations.

If a patient becomes pregnant while taking paroxetine, she should be advised of the potential harm to the fetus. Unless the benefits of paroxetine to the mother justify continuing treatment, consideration should be given to either discontinuing paroxetine therapy or switching to another antidepressant (see PRECAUTIONS: Discontinuation of Treatment With PAXIL CR). For women who intend to become pregnant or are in their first trimester of pregnancy, paroxetine should only be initiated after consideration of the other available treatment options.

Animal Findings

Reproduction studies were performed at doses up to 50 mg/kg/day in rats and 6 mg/kg/day in rabbits administered during organogenesis. These doses are approximately 8 (rat) and 2 (rabbit) times the maximum recommended human dose (MRHD) on an mg/m^2 basis. These studies have revealed no evidence of teratogenic effects. However, in rats, there was an increase in pup deaths during the first 4 days of lactation when dosing occurred during the last trimester of gestation and continued throughout lactation. This effect occurred at a dose of 1 mg/kg/day or approximately one-sixth of the MRHD on an mg/m^2 basis. The no-effect dose for rat pup mortality was not determined. The cause of these deaths is not known.

Nonteratogenic Effects

Neonates exposed to PAXIL CR and other SSRIs or serotonin and norepinephrine reuptake inhibitors (SNRIs), late in the third trimester have developed complications requiring prolonged hospitalization, respiratory support, and tube feeding. Such complications can arise immediately upon delivery. Reported clinical findings have included respiratory distress, cyanosis, apnea, seizures, temperature instability, feeding difficulty, vomiting, hypoglycemia, hypotonia, hypertonia, hyperreflexia, tremor, jitteriness, irritability, and constant crying. These features are consistent with either a direct toxic effect of SSRIs and SNRIs or, possibly, a drug discontinuation syndrome. It should be noted that, in some cases, the clinical picture is consistent with serotonin syndrome (see WARNINGS: Serotonin Syndrome or Neuroleptic Malignant Syndrome (NMS)-like Reactions).

Infants exposed to SSRIs in late pregnancy may have an increased risk for persistent pulmonary hypertension of the newborn (PPHN). PPHN occurs in 1 – 2 per 1,000 live births in the general population and is associated with substantial neonatal morbidity and mortality. In a retrospective case-control study of 377 women whose infants were born with PPHN and 836 women whose infants were born healthy, the risk for developing PPHN was approximately six-fold higher for infants exposed to SSRIs after the 20th week of gestation compared to infants who had not been exposed to antidepressants during pregnancy. There is currently no corroborative evidence regarding the risk for PPHN following exposure to SSRIs in pregnancy; this is the first study that has investigated the potential risk. The study did not include enough cases with exposure to individual SSRIs to determine if all SSRIs posed similar levels of PPHN risk.

There have also been postmarketing reports of premature births in pregnant women exposed to paroxetine or other SSRIs.

When treating a pregnant woman with paroxetine during the third trimester, the physician should carefully consider both the potential risks and benefits of treatment (see DOSAGE AND ADMINISTRATION). Physicians should note that in a prospective longitudinal study of 201 women with a history of major depression who were euthymic at the beginning of pregnancy, women who discontinued antidepressant medication during pregnancy were more likely to experience a relapse of major depression than women who continued antidepressant medication.

PRECAUTIONS

General

Activation of Mania/Hypomania

During premarketing testing of immediate-release paroxetine hydrochloride, hypomania or mania occurred in approximately 1.0% of paroxetine-treated unipolar patients compared to 1.1% of active-control and 0.3% of placebo-treated unipolar patients. In a subset of patients classified as bipolar, the rate of manic episodes was 2.2% for immediate-release paroxetine and 11.6% for the combined active-control groups. Among 1,627 patients with major depressive disorder, panic disorder, social anxiety disorder, or PMDD treated with PAXIL CR in controlled clinical studies, there were no reports of mania or hypomania. As with all drugs effective in the treatment of major depressive disorder, PAXIL CR should be used cautiously in patients with a history of mania.

Seizures

During premarketing testing of immediate-release paroxetine hydrochloride, seizures occurred in 0.1% of paroxetine-treated patients, a rate similar to that associated with other drugs effective in the treatment of major depressive disorder. Among 1,627 patients who received PAXIL CR in controlled clinical trials in major depressive disorder, panic disorder, social anxiety disorder, or PMDD, 1 patient (0.1%) experienced a seizure. PAXIL CR should be used cautiously in patients with a history of seizures. It should be discontinued in any patient who develops seizures.

Discontinuation of Treatment With PAXIL CR

Adverse events while discontinuing therapy with PAXIL CR were not systematically evaluated in most clinical trials; however, in recent placebo-controlled clinical trials utilizing daily doses of PAXIL CR up to 37.5 mg/day, spontaneously reported adverse events while discontinuing therapy with PAXIL CR were evaluated. Patients receiving 37.5 mg/day underwent an incremental decrease in the daily dose by 12.5 mg/day to a dose of 25 mg/day for 1 week before treatment was stopped. For patients receiving 25 mg/day or 12.5 mg/day, treatment was stopped without an incremental decrease in dose. With this regimen in those studies, the following adverse events were reported for PAXIL CR, at an incidence of 2% or greater for PAXIL CR and were at least twice that reported for placebo: Dizziness, nausea, nervousness, and additional symptoms described by the investigator as associated with tapering or discontinuing PAXIL CR (e.g., emotional lability, headache, agitation, electric shock sensations, fatigue, and sleep disturbances). These events were reported as serious in 0.3% of patients who discontinued therapy with PAXIL CR.

During marketing of PAXIL CR and other SSRIs and SNRIs, there have been spontaneous reports of adverse events occurring upon discontinuation of these drugs, (particularly when abrupt), including the following: Dysphoric mood, irritability, agitation, dizziness, sensory disturbances (e.g., paresthesias such as electric shock sensations and tinnitus), anxiety, confusion, headache, lethargy, emotional lability, insomnia, and hypomania. While these events are generally self-limiting, there have been reports of serious discontinuation symptoms.

Patients should be monitored for these symptoms when discontinuing treatment with PAXIL CR. A gradual reduction in the dose rather than abrupt cessation is recommended whenever possible. If intolerable symptoms occur following a decrease in the dose or upon discontinuation of treatment, then resuming the previously prescribed dose may be considered. Subsequently, the physician may continue decreasing the dose but at a more gradual rate (see DOSAGE AND ADMINISTRATION).

See also PRECAUTIONS: Pediatric Use, for adverse events reported upon discontinuation of treatment with paroxetine in pediatric patients.

Tamoxifen

Some studies have shown that the efficacy of tamoxifen, as measured by the risk of breast cancer relapse/mortality, may be reduced when co-prescribed with paroxetine as a result of paroxetine’s irreversible inhibition of CYP2D6 (see Drug Interactions). However, other studies have failed to demonstrate such a risk. It is uncertain whether the coadministration of paroxetine and tamoxifen has a significant adverse effect on the efficacy of tamoxifen. One study suggests that the risk may increase with longer duration of coadministration. When tamoxifen is used for the treatment or prevention of breast cancer, prescribers should consider using an alternative antidepressant with little or no CYP2D6 inhibition.

Akathisia

The use of paroxetine or other SSRIs has been associated with the development of akathisia, which is characterized by an inner sense of restlessness and psychomotor agitation such as an inability to sit or stand still usually associated with subjective distress. This is most likely to occur within the first few weeks of treatment.

Hyponatremia

Hyponatremia may occur as a result of treatment with SSRIs and SNRIs, including PAXIL CR. In many cases, this hyponatremia appears to be the result of the syndrome of inappropriate antidiuretic hormone secretion (SIADH). Cases with serum sodium lower than 110 mmol/L have been reported. Elderly patients may be at greater risk of developing hyponatremia with SSRIs and SNRIs. Also, patients taking diuretics or who are otherwise volume depleted may be at greater risk (see PRECAUTIONS: Geriatric Use). Discontinuation of PAXIL CR should be considered in patients with symptomatic hyponatremia and appropriate medical intervention should be instituted.

Signs and symptoms of hyponatremia include headache, difficulty concentrating, memory impairment, confusion, weakness, and unsteadiness, which may lead to falls. Signs and symptoms associated with more severe and/or acute cases have included hallucination, syncope, seizure, coma, respiratory arrest, and death.

Abnormal Bleeding

SSRIs and SNRIs, including paroxetine, may increase the risk of bleeding events. Concomitant use of aspirin, nonsteroidal anti-inflammatory drugs, warfarin, and other anticoagulants may add to this risk. Case reports and epidemiological studies (case-control and cohort design) have demonstrated an association between use of drugs that interfere with serotonin reuptake and the occurrence of gastrointestinal bleeding. Bleeding events related to SSRIs and SNRIs use have ranged from ecchymoses, hematomas, epistaxis, and petechiae to life-threatening hemorrhages. Patients should be cautioned about the risk of bleeding associated with the concomitant use of paroxetine and NSAIDs, aspirin, or other drugs that affect coagulation.

Bone Fracture

Epidemiological studies on bone fracture risk following exposure to some antidepressants, including SSRIs, have reported an association between antidepressant treatment and fractures. There are multiple possible causes for this observation and it is unknown to what extent fracture risk is directly attributable to SSRI treatment. The possibility of a pathological fracture, that is, a fracture produced by minimal trauma in a patient with decreased bone mineral density, should be considered in patients treated with paroxetine who present with unexplained bone pain, point tenderness, swelling, or bruising.

Use in Patients With Concomitant Illness

Clinical experience with immediate-release paroxetine hydrochloride in patients with certain concomitant systemic illness is limited. Caution is advisable in using PAXIL CR in patients with diseases or conditions that could affect metabolism or hemodynamic responses.

As with other SSRIs, mydriasis has been infrequently reported in premarketing studies with paroxetine hydrochloride. A few cases of acute angle closure glaucoma associated with therapy with immediate-release paroxetine have been reported in the literature. As mydriasis can cause acute angle closure in patients with narrow angle glaucoma, caution should be used when PAXIL CR is prescribed for patients with narrow angle glaucoma.

PAXIL CR or the immediate-release formulation has not been evaluated or used to any appreciable extent in patients with a recent history of myocardial infarction or unstable heart disease. Patients with these diagnoses were excluded from clinical studies during premarket testing. Evaluation of electrocardiograms of 682 patients who received immediate-release paroxetine hydrochloride in double-blind, placebo-controlled trials, however, did not indicate that paroxetine is associated with the development of significant ECG abnormalities. Similarly, paroxetine hydrochloride does not cause any clinically important changes in heart rate or blood pressure.

Increased plasma concentrations of paroxetine occur in patients with severe renal impairment (creatinine clearance <30 mL/min.) or severe hepatic impairment. A lower starting dose should be used in such patients (see DOSAGE AND ADMINISTRATION).

Information for Patients

PAXIL CR should not be chewed or crushed, and should be swallowed whole.

Patients should be cautioned about the risk of serotonin syndrome with the concomitant use of PAXIL CR and triptans, tramadol, or other serotonergic agents.

Prescribers or other health professionals should inform patients, their families, and their caregivers about the benefits and risks associated with treatment with PAXIL CR and should counsel them in its appropriate use. A patient Medication Guide is available for PAXIL CR. The prescriber or health professional should instruct patients, their families, and their caregivers to read the Medication Guide and should assist them in understanding its contents. Patients should be given the opportunity to discuss the contents of the Medication Guide and to obtain answers to any questions they may have. The complete text of the Medication Guide is reprinted at the end of this document.

Patients should be advised of the following issues and asked to alert their prescriber if these occur while taking PAXIL CR.

Clinical Worsening and Suicide Risk

Patients, their families, and their caregivers should be encouraged to be alert to the emergence of anxiety, agitation, panic attacks, insomnia, irritability, hostility, aggressiveness, impulsivity, akathisia (psychomotor restlessness), hypomania, mania, other unusual changes in behavior, worsening of depression, and suicidal ideation, especially early during antidepressant treatment and when the dose is adjusted up or down. Families and caregivers of patients should be advised to look for the emergence of such symptoms on a day-to-day basis, since changes may be abrupt. Such symptoms should be reported to the patient’s prescriber or health professional, especially if they are severe, abrupt in onset, or were not part of the patient’s presenting symptoms. Symptoms such as these may be associated with an increased risk for suicidal thinking and behavior and indicate a need for very close monitoring and possibly changes in the medication.

Drugs That Interfere With Hemostasis (e.g., NSAIDs, Aspirin, and Warfarin)

Patients should be cautioned about the concomitant use of paroxetine and NSAIDs, aspirin, warfarin, or other drugs that affect coagulation since combined use of psychotropic drugs that interfere with serotonin reuptake and these agents has been associated with an increased risk of bleeding.

Interference With Cognitive and Motor Performance

Any psychoactive drug may impair judgment, thinking, or motor skills. Although in controlled studies immediate-release paroxetine hydrochloride has not been shown to impair psychomotor performance, patients should be cautioned about operating hazardous machinery, including automobiles, until they are reasonably certain that therapy with PAXIL CR does not affect their ability to engage in such activities.

Completing Course of Therapy

While patients may notice improvement with use of PAXIL CR in 1 to 4 weeks, they should be advised to continue therapy as directed.

Concomitant Medications

Patients should be advised to inform their physician if they are taking, or plan to take, any prescription or over-the-counter drugs, since there is a potential for interactions.

Alcohol

Although immediate-release paroxetine hydrochloride has not been shown to increase the impairment of mental and motor skills caused by alcohol, patients should be advised to avoid alcohol while taking PAXIL CR.

Pregnancy

Patients should be advised to notify their physician if they become pregnant or intend to become pregnant during therapy (see WARNINGS: Usage in Pregnancy: Teratogenic Effects and Nonteratogenic Effects).

Nursing

Patients should be advised to notify their physician if they are breastfeeding an infant (see PRECAUTIONS: Nursing Mothers).

Laboratory Tests

There are no specific laboratory tests recommended.

Drug Interactions

Tryptophan

As with other serotonin reuptake inhibitors, an interaction between paroxetine and tryptophan may occur when they are coadministered. Adverse experiences, consisting primarily of headache, nausea, sweating, and dizziness, have been reported when tryptophan was administered to patients taking immediate-release paroxetine. Consequently, concomitant use of PAXIL CR with tryptophan is not recommended (see WARNINGS: Serotonin Syndrome or Neuroleptic Malignant Syndrome (NMS)-like Reactions).

Monoamine Oxidase Inhibitors

See CONTRAINDICATIONS and WARNINGS.

Pimozide

In a controlled study of healthy volunteers, after immediate-release paroxetine hydrochloride was titrated to 60 mg daily, co-administration of a single dose of 2 mg pimozide was associated with mean increases in pimozide AUC of 151% and Cmax of 62%, compared to pimozide administered alone. The increase in pimozide AUC and Cmax is due to the CYP2D6 inhibitory properties of paroxetine. Due to the narrow therapeutic index of pimozide and its known ability to prolong the QT interval, concomitant use of pimozide and PAXIL CR is contraindicated (see CONTRAINDICATIONS).

Serotonergic Drugs

Based on the mechanism of action of SNRIs and SSRIs, including paroxetine hydrochloride, and the potential for serotonin syndrome, caution is advised when PAXIL CR is coadministered with other drugs that may affect the serotonergic neurotransmitter systems, such as triptans, lithium, fentanyl, tramadol, or St. John's Wort (see WARNINGS: Serotonin Syndrome or Neuroleptic Malignant Syndrome (NMS)-like Reactions). The concomitant use of PAXIL CR with MAOIs (including linezolid and methylene blue) is contraindicated (see CONTRAINDICATIONS). The concomitant use of PAXIL CR with other SSRIs, SNRIs or tryptophan is not recommended (see PRECAUTIONS: Drug Interactions, Tryptophan).

Thioridazine

See CONTRAINDICATIONS and WARNINGS.

Warfarin

Preliminary data suggest that there may be a pharmacodynamic interaction (that causes an increased bleeding diathesis in the face of unaltered prothrombin time) between paroxetine and warfarin. Since there is little clinical experience, the concomitant administration of PAXIL CR and warfarin should be undertaken with caution (see PRECAUTIONS: Drugs That Interfere With Hemostasis).

Triptans

There have been rare postmarketing reports of serotonin syndrome with the use of an SSRI and a triptan. If concomitant use of PAXIL CR with a triptan is clinically warranted, careful observation of the patient is advised, particularly during treatment initiation and dose increases (see WARNINGS: Serotonin Syndrome or Neuroleptic Malignant Syndrome (NMS)-like Reactions)

Drugs Affecting Hepatic Metabolism

The metabolism and pharmacokinetics of paroxetine may be affected by the induction or inhibition of drug-metabolizing enzymes.

Cimetidine

Cimetidine inhibits many cytochrome P450 (oxidative) enzymes. In a study where immediate-release paroxetine (30 mg once daily) was dosed orally for 4 weeks, steady-state plasma concentrations of paroxetine were increased by approximately 50% during coadministration with oral cimetidine (300 mg three times daily) for the final week. Therefore, when these drugs are administered concurrently, dosage adjustment of PAXIL CR after the starting dose should be guided by clinical effect. The effect of paroxetine on cimetidine’s pharmacokinetics was not studied.

Phenobarbital

Phenobarbital induces many cytochrome P450 (oxidative) enzymes. When a single oral 30-mg dose of immediate-release paroxetine was administered at phenobarbital steady state (100 mg once daily for 14 days), paroxetine AUC and T½ were reduced (by an average of 25% and 38%, respectively) compared to paroxetine administered alone. The effect of paroxetine on phenobarbital pharmacokinetics was not studied. Since paroxetine exhibits nonlinear pharmacokinetics, the results of this study may not address the case where the 2 drugs are both being chronically dosed. No initial dosage adjustment with PAXIL CR is considered necessary when coadministered with phenobarbital; any subsequent adjustment should be guided by clinical effect.

Phenytoin

When a single oral 30-mg dose of immediate-release paroxetine was administered at phenytoin steady state (300 mg once daily for 14 days), paroxetine AUC and T½ were reduced (by an average of 50% and 35%, respectively) compared to immediate-release paroxetine administered alone. In a separate study, when a single oral 300-mg dose of phenytoin was administered at paroxetine steady state (30 mg once daily for 14 days), phenytoin AUC was slightly reduced (12% on average) compared to phenytoin administered alone. Since both drugs exhibit nonlinear pharmacokinetics, the above studies may not address the case where the 2 drugs are both being chronically dosed. No initial dosage adjustments are considered necessary when PAXIL CR is coadministered with phenytoin; any subsequent adjustments should be guided by clinical effect (see ADVERSE REACTIONS: Postmarketing Reports).

Drugs Metabolized by CYP2D6

Many drugs, including most drugs effective in the treatment of major depressive disorder (paroxetine, other SSRIs, and many tricyclics), are metabolized by the cytochrome P450 isozyme CYP2D6. Like other agents that are metabolized by CYP2D6, paroxetine may significantly inhibit the activity of this isozyme. In most patients (>90%), this CYP2D6 isozyme is saturated early during paroxetine dosing. In 1 study, daily dosing of immediate-release paroxetine (20 mg once daily) under steady-state conditions increased single-dose desipramine (100 mg) Cmax, AUC, and T½ by an average of approximately 2-, 5-, and 3-fold, respectively. Concomitant use of paroxetine with risperidone, a CYP2D6 substrate has also been evaluated. In 1 study, daily dosing of paroxetine 20 mg in patients stabilized on risperidone (4 to 8 mg/day) increased mean plasma concentrations of risperidone approximately 4-fold, decreased 9-hydroxyrisperidone concentrations approximately 10%, and increased concentrations of the active moiety (the sum of risperidone plus 9-hydroxyrisperidone) approximately 1.4-fold. The effect of paroxetine on the pharmacokinetics of atomoxetine has been evaluated when both drugs were at steady state. In healthy volunteers who were extensive metabolizers of CYP2D6, paroxetine 20 mg daily was given in combination with 20 mg atomoxetine every 12 hours. This resulted in increases in steady state atomoxetine AUC values that were 6- to 8-fold greater and in atomoxetine Cmax values that were 3- to 4-fold greater than when atomoxetine was given alone. Dosage adjustment of atomoxetine may be necessary and it is recommended that atomoxetine be initiated at a reduced dose when given with paroxetine.

Concomitant use of PAXIL CR with other drugs metabolized by cytochrome CYP2D6 has not been formally studied but may require lower doses than usually prescribed for either PAXIL CR or the other drug.

Therefore, coadministration of PAXIL CR with other drugs that are metabolized by this isozyme, including certain drugs effective in the treatment of major depressive disorder (e.g., nortriptyline, amitriptyline, imipramine, desipramine, and fluoxetine), phenothiazines, risperidone, and Type 1C antiarrhythmics (e.g., propafenone, flecainide, and encainide), or that inhibit this enzyme (e.g., quinidine), should be approached with caution.

However, due to the risk of serious ventricular arrhythmias and sudden death potentially associated with elevated plasma levels of thioridazine, paroxetine and thioridazine should not be coadministered (see CONTRAINDICATIONS and WARNINGS).

Tamoxifen is a pro-drug requiring metabolic activation by CYP2D6. Inhibition of CYP2D6 by paroxetine may lead to reduced plasma concentrations of an active metabolite (endoxifen) and hence reduced efficacy of tamoxifen (see PRECAUTIONS).

At steady state, when the CYP2D6 pathway is essentially saturated, paroxetine clearance is governed by alternative P450 isozymes that, unlike CYP2D6, show no evidence of saturation (see PRECAUTIONS: Tricyclic Antidepressants [TCAs]).

Drugs Metabolized by Cytochrome CYP3A4

An in vivo interaction study involving the coadministration under steady-state conditions of paroxetine and terfenadine, a substrate for CYP3A4, revealed no effect of paroxetine on terfenadine pharmacokinetics. In addition, in vitro studies have shown ketoconazole, a potent inhibitor of CYP3A4 activity, to be at least 100 times more potent than paroxetine as an inhibitor of the metabolism of several substrates for this enzyme, including terfenadine, astemizole, cisapride, triazolam, and cyclosporine. Based on the assumption that the relationship between paroxetine’s in vitro Ki and its lack of effect on terfenadine's in vivo clearance predicts its effect on other CYP3A4 substrates, paroxetine’s extent of inhibition of CYP3A4 activity is not likely to be of clinical significance.

Tricyclic Antidepressants (TCAs)

Caution is indicated in the coadministration of TCAs with PAXIL CR, because paroxetine may inhibit TCA metabolism. Plasma TCA concentrations may need to be monitored, and the dose of TCA may need to be reduced, if a TCA is coadministered with PAXIL CR (see PRECAUTIONS: Drugs Metabolized by Cytochrome CYP2D6).

Drugs Highly Bound to Plasma Protein

Because paroxetine is highly bound to plasma protein, administration of PAXIL CR to a patient taking another drug that is highly protein bound may cause increased free concentrations of the other drug, potentially resulting in adverse events. Conversely, adverse effects could result from displacement of paroxetine by other highly bound drugs.

Drugs That Interfere With Hemostasis (e.g., NSAIDs, Aspirin, and Warfarin)

Serotonin release by platelets plays an important role in hemostasis. Epidemiological studies of the case-control and cohort design that have demonstrated an association between use of psychotropic drugs that interfere with serotonin reuptake and the occurrence of upper gastrointestinal bleeding have also shown that concurrent use of an NSAID or aspirin may potentiate this risk of bleeding. Altered anticoagulant effects, including increased bleeding, have been reported when SSRIs or SNRIs are coadministered with warfarin. Patients receiving warfarin therapy should be carefully monitored when paroxetine is initiated or discontinued.

Alcohol

Although paroxetine does not increase the impairment of mental and motor skills caused by alcohol, patients should be advised to avoid alcohol while taking PAXIL CR.

Lithium

A multiple-dose study with immediate-release paroxetine hydrochloride has shown that there is no pharmacokinetic interaction between paroxetine and lithium carbonate. However, due to the potential for serotonin syndrome, caution is advised when immediate-release paroxetine hydrochloride is coadministered with lithium.

Digoxin

The steady-state pharmacokinetics of paroxetine was not altered when administered with digoxin at steady state. Mean digoxin AUC at steady state decreased by 15% in the presence of paroxetine. Since there is little clinical experience, the concurrent administration of PAXIL CR and digoxin should be undertaken with caution.

Diazepam

Under steady-state conditions, diazepam does not appear to affect paroxetine kinetics. The effects of paroxetine on diazepam were not evaluated.

Procyclidine

Daily oral dosing of immediate-release paroxetine (30 mg once daily) increased steady-state AUC0-24, Cmax, and Cmin values of procyclidine (5 mg oral once daily) by 35%, 37%, and 67%, respectively, compared to procyclidine alone at steady state. If anticholinergic effects are seen, the dose of procyclidine should be reduced.

Beta-Blockers

In a study where propranolol (80 mg twice daily) was dosed orally for 18 days, the established steady-state plasma concentrations of propranolol were unaltered during coadministration with immediate-release paroxetine (30 mg once daily) for the final 10 days. The effects of propranolol on paroxetine have not been evaluated (see ADVERSE REACTIONS: Postmarketing Reports).

Theophylline

Reports of elevated theophylline levels associated with immediate-release paroxetine treatment have been reported. While this interaction has not been formally studied, it is recommended that theophylline levels be monitored when these drugs are concurrently administered.

Fosamprenavir/Ritonavir

Co-administration of fosamprenavir/ritonavir with paroxetine significantly decreased plasma levels of paroxetine. Any dose adjustment should be guided by clinical effect (tolerability and efficacy).

Electroconvulsive Therapy (ECT)

There are no clinical studies of the combined use of ECT and PAXIL CR.

Carcinogenesis, Mutagenesis, Impairment of Fertility

Carcinogenesis

Two-year carcinogenicity studies were conducted in rodents given paroxetine in the diet at 1, 5, and 25 mg/kg/day (mice) and 1, 5, and 20 mg/kg/day (rats). These doses are up to approximately 2 (mouse) and 3 (rat) times the MRHD on a mg/m^2 basis. There was a significantly greater number of male rats in the high-dose group with reticulum cell sarcomas (1/100, 0/50, 0/50, and 4/50 for control, low-, middle-, and high-dose groups, respectively) and a significantly increased linear trend across dose groups for the occurrence of lymphoreticular tumors in male rats. Female rats were not affected. Although there was a dose-related increase in the number of tumors in mice, there was no drug-related increase in the number of mice with tumors. The relevance of these findings to humans is unknown.

Mutagenesis

Paroxetine produced no genotoxic effects in a battery of 5 in vitro and 2 in vivo assays that included the following: Bacterial mutation assay, mouse lymphoma mutation assay, unscheduled DNA synthesis assay, and tests for cytogenetic aberrations in vivo in mouse bone marrow and in vitro in human lymphocytes and in a dominant lethal test in rats.

Impairment of Fertility

Some clinical studies have shown that SSRIs (including paroxetine) may affect sperm quality during SSRI treatment, which may affect fertility in some men.

A reduced pregnancy rate was found in reproduction studies in rats at a dose of paroxetine of 15 mg/kg/day, which is approximately twice the MRHD on a mg/m^2 basis. Irreversible lesions occurred in the reproductive tract of male rats after dosing in toxicity studies for 2 to 52 weeks. These lesions consisted of vacuolation of epididymal tubular epithelium at 50 mg/kg/day and atrophic changes in the seminiferous tubules of the testes with arrested spermatogenesis at 25 mg/kg/day (approximately 8 and 4 times the MRHD on a mg/m^2 basis).

Pregnancy

Pregnancy Category D. See WARNINGS: Usage in Pregnancy: Teratogenic Effects and Nonteratogenic Effects.

Labor and Delivery

The effect of paroxetine on labor and delivery in humans is unknown.

Nursing Mothers

Like many other drugs, paroxetine is secreted in human milk, and caution should be exercised when PAXIL CR is administered to a nursing woman.

Pediatric Use

Safety and effectiveness in the pediatric population have not been established (see BOX WARNING and WARNINGS: Clinical Worsening and Suicide Risk). Three placebo-controlled trials in 752 pediatric patients with MDD have been conducted with immediate-release PAXIL, and the data were not sufficient to support a claim for use in pediatric patients. Anyone considering the use of PAXIL CR in a child or adolescent must balance the potential risks with the clinical need. Decreased appetite and weight loss have been observed in association with the use of SSRIs. Consequently, regular monitoring of weight and growth should be performed in children and adolescents treated with an SSRI such as PAXIL CR.

In placebo-controlled clinical trials conducted with pediatric patients, the following adverse events were reported in at least 2% of pediatric patients treated with immediate-release paroxetine hydrochloride and occurred at a rate at least twice that for pediatric patients receiving placebo: emotional lability (including self-harm, suicidal thoughts, attempted suicide, crying, and mood fluctuations), hostility, decreased appetite, tremor, sweating, hyperkinesia, and agitation.

Events reported upon discontinuation of treatment with immediate-release paroxetine hydrochloride in the pediatric clinical trials that included a taper phase regimen, which occurred in at least 2% of patients who received immediate-release paroxetine hydrochloride and which occurred at a rate at least twice that of placebo, were: emotional lability (including suicidal ideation, suicide attempt, mood changes, and tearfulness), nervousness, dizziness, nausea, and abdominal pain (see DOSAGE AND ADMINISTRATION: Discontinuation of Treatment With PAXIL CR).

Geriatric Use

SSRIs and SNRIs, including PAXIL CR, have been associated with cases of clinically significant hyponatremia in elderly patients, who may be at greater risk for this adverse event (see PRECAUTIONS: Hyponatremia).

In worldwide premarketing clinical trials with immediate-release paroxetine hydrochloride, 17% of paroxetine-treated patients (approximately 700) were 65 years or older. Pharmacokinetic studies revealed a decreased clearance in the elderly, and a lower starting dose is recommended; there were, however, no overall differences in the adverse event profile between elderly and younger patients, and effectiveness was similar in younger and older patients (see CLINICAL PHARMACOLOGY and DOSAGE AND ADMINISTRATION).

In a controlled study focusing specifically on elderly patients with major depressive disorder, PAXIL CR was demonstrated to be safe and effective in the treatment of elderly patients (>60 years) with major depressive disorder (see CLINICAL PHARMACOLOGY: Clinical Trials and ADVERSE REACTIONS: Table 3.)

ADVERSE REACTIONS

The information included under the “Adverse Findings Observed in Short-Term, Placebo-Controlled Trials With PAXIL CR” subsection of ADVERSE REACTIONS is based on data from 11 placebo-controlled clinical trials. Three of these studies were conducted in patients with major depressive disorder, 3 studies were done in patients with panic disorder, 1 study was conducted in patients with social anxiety disorder, and 4 studies were done in female patients with PMDD. Two of the studies in major depressive disorder, which enrolled patients in the age range 18 to 65 years, are pooled. Information from a third study of major depressive disorder, which focused on elderly patients (60 to 88 years), is presented separately as is the information from the panic disorder studies and the information from the PMDD studies. Information on additional adverse events associated with PAXIL CR and the immediate-release formulation of paroxetine hydrochloride is included in a separate subsection (see Other Events Observed During the Clinical Development of Paroxetine).

Adverse Events Associated With Discontinuation of Treatment

Major Depressive Disorder

Ten percent (21/212) of patients treated with PAXIL CR discontinued treatment due to an adverse event in a pool of 2 studies of patients with major depressive disorder. The most common events (≥1%) associated with discontinuation and considered to be drug related (i.e., those events associated with dropout at a rate approximately twice or greater for PAXIL CR compared to placebo) included the following:

 | PAXIL CR; (n = 212) | Placebo; (n = 211)
Nausea | 3.7% | 0.5%
Asthenia | 1.9% | 0.5%
Dizziness | 1.4% | 0.0%
Somnolence | 1.4% | 0.0%

In a placebo-controlled study of elderly patients with major depressive disorder, 13% (13/104) of patients treated with PAXIL CR discontinued due to an adverse event. Events meeting the above criteria included the following:

 | PAXIL CR; (n = 104) | Placebo; (n = 109)
Nausea | 2.9% | 0.0%
Headache | 1.9% | 0.9%
Depression | 1.9% | 0.0%
LFT’s abnormal | 1.9% | 0.0%

Panic Disorder

Eleven percent (50/444) of patients treated with PAXIL CR in panic disorder studies discontinued treatment due to an adverse event. Events meeting the above criteria included the following:

 | PAXIL CR; (n = 444) | Placebo; (n = 445)
Nausea | 2.9% | 0.4%
Insomnia | 1.8% | 0.0%
Headache | 1.4% | 0.2%
Asthenia | 1.1% | 0.0%

Social Anxiety Disorder

Three percent (5/186) of patients treated with PAXIL CR in the social anxiety disorder study discontinued treatment due to an adverse event. Events meeting the above criteria included the following:

 | PAXIL CR; (n = 186) | Placebo; (n = 184)
Nausea | 2.2% | 0.5%
Headache | 1.6% | 0.5%
Diarrhea | 1.1% | 0.5%

Premenstrual Dysphoric Disorder

Spontaneously reported adverse events were monitored in studies of both continuous and intermittent dosing of PAXIL CR in the treatment of PMDD. Generally, there were few differences in the adverse event profiles of the 2 dosing regimens. Thirteen percent (88/681) of patients treated with PAXIL CR in PMDD studies of continuous dosing discontinued treatment due to an adverse event.

The most common events (≥1%) associated with discontinuation in either group treated with PAXIL CR with an incidence rate that is at least twice that of placebo in PMDD trials that employed a continuous dosing regimen are shown in the following table. This table also shows those events that were dose dependent (indicated with an asterisk) as defined as events having an incidence rate with 25 mg of PAXIL CR that was at least twice that with 12.5 mg of PAXIL CR (as well as the placebo group).

 | PAXIL CR; 25 mg; (n = 348) | PAXIL CR; 12.5 mg; (n = 333) | Placebo; (n = 349)
TOTAL | 15% | 9.9% | 6.3%
Nauseaa | 6.0% | 2.4% | 0.9%
Asthenia | 4.9% | 3.0% | 1.4%
Somnolencea | 4.3% | 1.8% | 0.3%
Insomnia | 2.3% | 1.5% | 0.0%
Concentration Impaireda | 2.0% | 0.6% | 0.3%
Dry moutha | 2.0% | 0.6% | 0.3%
Dizzinessa | 1.7% | 0.6% | 0.6%
Decreased Appetitea | 1.4% | 0.6% | 0.0%
Sweatinga | 1.4% | 0.0% | 0.3%
Tremora | 1.4% | 0.3% | 0.0%
Yawna | 1.1% | 0.0% | 0.0%
Diarrhea | 0.9% | 1.2% | 0.0%

a. Events considered to be dose dependent are defined as events having an incidence rate with 25 mg of PAXIL CR that was at least twice that with 12.5 mg of PAXIL CR (as well as the placebo group).

Commonly Observed Adverse Events

Major Depressive Disorder

The most commonly observed adverse events associated with the use of PAXIL CR in a pool of 2 trials (incidence of 5.0% or greater and incidence for PAXIL CR at least twice that for placebo, derived from Table 2) were: Abnormal ejaculation, abnormal vision, constipation, decreased libido, diarrhea, dizziness, female genital disorders, nausea, somnolence, sweating, trauma, tremor, and yawning.

Using the same criteria, the adverse events associated with the use of PAXIL CR in a study of elderly patients with major depressive disorder were: Abnormal ejaculation, constipation, decreased appetite, dry mouth, impotence, infection, libido decreased, sweating, and tremor.

Panic Disorder

In the pool of panic disorder studies, the adverse events meeting these criteria were: Abnormal ejaculation, somnolence, impotence, libido decreased, tremor, sweating, and female genital disorders (generally anorgasmia or difficulty achieving orgasm).

Social Anxiety Disorder

In the social anxiety disorder study, the adverse events meeting these criteria were: Nausea, asthenia, abnormal ejaculation, sweating, somnolence, impotence, insomnia, and libido decreased.

Premenstrual Dysphoric Disorder

The most commonly observed adverse events associated with the use of PAXIL CR either during continuous dosing or luteal phase dosing (incidence of 5% or greater and incidence for PAXIL CR at least twice that for placebo, derived from Table 6) were: Nausea, asthenia, libido decreased, somnolence, insomnia, female genital disorders, sweating, dizziness, diarrhea, and constipation.

In the luteal phase dosing PMDD trial, which employed dosing of 12.5 mg/day or 25 mg/day of PAXIL CR limited to the 2 weeks prior to the onset of menses over 3 consecutive menstrual cycles, adverse events were evaluated during the first 14 days of each off-drug phase. When the 3 off-drug phases were combined, the following adverse events were reported at an incidence of 2% or greater for PAXIL CR and were at least twice the rate of that reported for placebo: Infection (5.3% versus 2.5%), depression (2.8% versus 0.8%), insomnia (2.4% versus 0.8%), sinusitis (2.4% versus 0%), and asthenia (2.0% versus 0.8%).

Incidence in Controlled Clinical Trials

Table 2 enumerates adverse events that occurred at an incidence of 1% or more among patients treated with PAXIL CR, aged 18 to 65, who participated in 2 short-term (12-week) placebo-controlled trials in major depressive disorder in which patients were dosed in a range of 25 mg to 62.5 mg/day. Table 3 enumerates adverse events reported at an incidence of 5% or greater among elderly patients (ages 60 to 88) treated with PAXIL CR who participated in a short-term (12-week) placebo-controlled trial in major depressive disorder in which patients were dosed in a range of 12.5 mg to 50 mg/day. Table 4 enumerates adverse events reported at an incidence of 1% or greater among patients (19 to 72 years) treated with PAXIL CR who participated in short-term (10-week) placebo-controlled trials in panic disorder in which patients were dosed in a range of 12.5 mg to 75 mg/day. Table 5 enumerates adverse events reported at an incidence of 1% or greater among adult patients treated with PAXIL CR who participated in a short-term (12-week), double-blind, placebo-controlled trial in social anxiety disorder in which patients were dosed in a range of 12.5 to 37.5 mg/day. Table 6 enumerates adverse events that occurred at an incidence of 1% or more among patients treated with PAXIL CR who participated in three, 12-week, placebo-controlled trials in PMDD in which patients were dosed at 12.5 mg/day or 25 mg/day and in one 12-week placebo-controlled trial in which patients were dosed for 2 weeks prior to the onset of menses (luteal phase dosing) at 12.5 mg/day or 25 mg/day. Reported adverse events were classified using a standard COSTART-based Dictionary terminology.

The prescriber should be aware that these figures cannot be used to predict the incidence of side effects in the course of usual medical practice where patient characteristics and other factors differ from those that prevailed in the clinical trials. Similarly, the cited frequencies cannot be compared with figures obtained from other clinical investigations involving different treatments, uses, and investigators. The cited figures, however, do provide the prescribing physician with some basis for estimating the relative contribution of drug and nondrug factors to the side effect incidence rate in the population studied.

Table 2. Treatment-Emergent Adverse Events Occurring in ≥1% of Patients Treated With PAXIL CR in a Pool of 2 Studies in Major Depressive Disordera,b
Body System/Adverse Event | % Reporting Event
Body System/Adverse Event | PAXIL CR; (n = 212) | Placebo; (n = 211)
Body as a Whole
Headache | 27% | 20%
Asthenia | 14% | 9%
Infectionc | 8% | 5%
Abdominal Pain | 7% | 4%
Back Pain | 5% | 3%
Traumad | 5% | 1%
Paine | 3% | 1%
Allergic Reactionf | 2% | 1%
Cardiovascular System
Tachycardia | 1% | 0%
Vasodilatationg | 2% | 0%
Digestive System
Nausea | 22% | 10%
Diarrhea | 18% | 7%
Dry Mouth | 15% | 8%
Constipation | 10% | 4%
Flatulence | 6% | 4%
Decreased Appetite | 4% | 2%
Vomiting | 2% | 1%
Nervous System
Somnolence | 22% | 8%
Insomnia | 17% | 9%
Dizziness | 14% | 4%
Libido Decreased | 7% | 3%
Tremor | 7% | 1%
Hypertonia | 3% | 1%
Paresthesia | 3% | 1%
Agitation | 2% | 1%
Confusion | 1% | 0%
Respiratory System
Yawn | 5% | 0%
Rhinitis | 4% | 1%
Cough Increased | 2% | 1%
Bronchitis | 1% | 0%
Skin and Appendages
Sweating | 6% | 2%
Photosensitivity | 2% | 0%
Special Senses
Abnormal Visionh | 5% | 1%
Taste Perversion | 2% | 0%
Urogenital System
Abnormal Ejaculationi,j | 26% | 1%
Female Genital Disorderi,k | 10% | <1%
Impotencei | 5% | 3%
Urinary Tract Infection | 3% | 1%
Menstrual Disorderi | 2% | <1%
Vaginitisi | 2% | 0%

a. Adverse events for which the PAXIL CR reporting incidence was less than or equal to the placebo incidence are not included. These events are: Abnormal dreams, anxiety, arthralgia, depersonalization, dysmenorrhea, dyspepsia, hyperkinesia, increased appetite, myalgia, nervousness, pharyngitis, purpura, rash, respiratory disorder, sinusitis, urinary frequency, and weight gain.

b. <1% means greater than zero and less than 1%.

c. Mostly flu.

d. A wide variety of injuries with no obvious pattern.

e. Pain in a variety of locations with no obvious pattern.

f. Most frequently seasonal allergic symptoms.

g. Usually flushing.

h. Mostly blurred vision.

i. Based on the number of males or females.

j. Mostly anorgasmia or delayed ejaculation.

k. Mostly anorgasmia or delayed orgasm.

Table 3. Treatment-Emergent Adverse Events Occurring in ≥5% of Patients Treated With PAXIL CR in a Study of Elderly Patients With Major Depressive Disordera,b
Body System/Adverse Event | % Reporting Event
Body System/Adverse Event | PAXIL CR; (n = 104) | Placebo; (n = 109)
Body as a Whole
Headache | 17% | 13%
Asthenia | 15% | 14%
Trauma | 8% | 5%
Infection | 6% | 2%
Digestive System
Dry Mouth | 18% | 7%
Diarrhea | 15% | 9%
Constipation | 13% | 5%
Dyspepsia | 13% | 10%
Decreased Appetite | 12% | 5%
Flatulence | 8% | 7%
Nervous System
Somnolence | 21% | 12%
Insomnia | 10% | 8%
Dizziness | 9% | 5%
Libido Decreased | 8% | <1%
Tremor | 7% | 0%
Skin and Appendages
Sweating | 10% | <1%
Urogenital System
Abnormal Ejaculationc,d | 17% | 3%
Impotencec | 9% | 3%

a. Adverse events for which the PAXIL CR reporting incidence was less than or equal to the placebo incidence are not included. These events are nausea and respiratory disorder.

b. <1% means greater than zero and less than 1%.

c. Based on the number of males.

d. Mostly anorgasmia or delayed ejaculation.

Table 4. Treatment-Emergent Adverse Events Occurring in ≥1% of Patients Treated With PAXIL CR in a Pool of 3 Panic Disorder Studiesa,b
Body System/Adverse Event | % Reporting Event
Body System/Adverse Event | PAXIL CR; (n = 444) | Placebo; (n = 445)
Body as a Whole
Asthenia | 15% | 10%
Abdominal Pain | 6% | 4%
Traumac | 5% | 4%
Cardiovascular System
Vasodilationd | 3% | 2%
Digestive System
Nausea | 23% | 17%
Dry Mouth | 13% | 9%
Diarrhea | 12% | 9%
Constipation | 9% | 6%
Decreased Appetite | 8% | 6%
Metabolic/Nutritional Disorders
Weight Loss | 1% | 0%
Musculoskeletal System
Myalgia | 5% | 3%
Nervous System
Insomnia | 20% | 11%
Somnolence | 20% | 9%
Libido Decreased | 9% | 4%
Nervousness | 8% | 7%
Tremor | 8% | 2%
Anxiety | 5% | 4%
Agitation | 3% | 2%
Hypertoniae | 2% | <1%
Myoclonus | 2% | <1%
Respiratory System
Sinusitis | 8% | 5%
Yawn | 3% | 0%
Skin and Appendages
Sweating | 7% | 2%
Special Senses
Abnormal Visionf | 3% | <1%
Urogenital System
Abnormal Ejaculationg,h | 27% | 3%
Impotenceg | 10% | 1%
Female Genital Disordersi,j | 7% | 1%
Urinary Frequency | 2% | <1%
Urination Impaired | 2% | <1%
Vaginitisi | 1% | <1%

a. Adverse events for which the reporting rate for PAXIL CR was less than or equal to the placebo rate are not included. These events are: Abnormal dreams, allergic reaction, back pain, bronchitis, chest pain, concentration impaired, confusion, cough increased, depression, dizziness, dysmenorrhea, dyspepsia, fever, flatulence, headache, increased appetite, infection, menstrual disorder, migraine, pain, paresthesia, pharyngitis, respiratory disorder, rhinitis, tachycardia, taste perversion, thinking abnormal, urinary tract infection, and vomiting.

b. < 1% means greater than zero and less than 1%.

c. Various physical injuries.

d. Mostly flushing.

e. Mostly muscle tightness or stiffness.

f. Mostly blurred vision.

g. Based on the number of male patients.

h. Mostly anorgasmia or delayed ejaculation.

i. Based on the number of female patients.

j. Mostly anorgasmia or difficulty achieving orgasm.

Table 5. Treatment-Emergent Adverse Effects Occurring in ≥1% of Patients Treated With PAXIL CR in a Social Anxiety Disorder Studya,b
Body System/Adverse Event | % Reporting Event
Body System/Adverse Event | PAXIL CR; (n = 186) | Placebo; (n = 184)
Body as a Whole
Headache | 23% | 17%
Asthenia | 18% | 7%
Abdominal Pain | 5% | 4%
Back Pain | 4% | 1%
Traumac | 3% | <1%
Allergic Reactiond | 2% | <1%
Chest Pain | 1% | <1%
Cardiovascular System
Hypertension | 2% | 0%
Migraine | 2% | 1%
Tachycardia | 2% | 1%
Digestive System
Nausea | 22% | 6%
Diarrhea | 9% | 8%
Constipation | 5% | 2%
Dry Mouth | 3% | 2%
Dyspepsia | 2% | <1%
Decreased Appetite | 1% | <1%
Tooth Disorder | 1% | 0%
Metabolic/Nutritional Disorders
Weight Gain | 3% | 1%
Weight Loss | 1% | 0%
Nervous System
Insomnia | 9% | 4%
Somnolence | 9% | 4%
Libido Decreased | 8% | 1%
Dizziness | 7% | 4%
Tremor | 4% | 2%
Anxiety | 2% | 1%
Concentration Impaired | 2% | 0%
Depression | 2% | 1%
Myoclonus | 1% | <1%
Paresthesia | 1% | <1%
Respiratory System
Yawn | 2% | 0%
Skin and Appendages
Sweating | 14% | 3%
Eczema | 1% | 0%
Special Senses
Abnormal Visione | 2% | 0%
Abnormality of Accommodation | 2% | 0%
Urogenital System
Abnormal Ejaculationf,g | 15% | 1%
Impotencef | 9% | 0%
Female Genital Disordersh,i | 3% | 0%

a. Adverse events for which the reporting rate for PAXIL CR was less than or equal to the placebo rate are not included. These events are: Dysmenorrhea, flatulence, gastroenteritis, hypertonia, infection, pain, pharyngitis, rash, respiratory disorder, rhinitis, and vomiting.

b. <1% means greater than zero and less than 1%.

c. Various physical injuries.

d. Most frequently seasonal allergic symptoms.

e. Mostly blurred vision.

f. Based on the number of male patients.

g. Mostly anorgasmia or delayed ejaculation.

h. Based on the number of female patients.

i. Mostly anorgasmia or difficulty achieving orgasm.

Table 6. Treatment-Emergent Adverse Events Occurring in ≥1% of Patients Treated With PAXIL CR in a Pool of 3 Premenstrual Dysphoric Disorder Studies With Continuous Dosing or in 1 Premenstrual Dysphoric Disorder Study With Luteal Phase Dosinga,b,c
Body System/Adverse Event | % Reporting Event
Body System/Adverse Event | Continuous Dosing |  | Luteal Phase Dosing
Body System/Adverse Event | PAXIL CR; (n = 681) | Placebo; (n = 349) | PAXIL CR; (n = 246) | Placebo; (n = 120)
Body as a Whole
Asthenia | 17% | 6% | 15% | 4%
Headache | 15% | 12% | - | -
Infection | 6% | 4% | - | -
Abdominal pain | - | - | 3% | 0%
Cardiovascular System
Migraine | 1% | <1% | - | -
Digestive System
Nausea | 17% | 7% | 18% | 2%
Diarrhea | 6% | 2% | 6% | 0%
Constipation | 5% | 1% | 2% | <1%
Dry Mouth | 4% | 2% | 2% | <1%
Increased Appetite | 3% | <1% | - | -
Decreased Appetite | 2% | <1% | 2% | 0%
Dyspepsia | 2% | 1% | 2% | 2%
Gingivitis | - | - | 1% | 0%
Metabolic and Nutritional Disorders
Generalized Edema | - | - | 1% | <1%
Weight Gain | - | - | 1% | <1%
Musculoskeletal System
Arthralgia | 2% | 1% | - | -
Nervous System
Libido Decreased | 12% | 5% | 9% | 6%
Somnolence | 9% | 2% | 3% | <1%
Insomnia | 8% | 2% | 7% | 3%
Dizziness | 7% | 3% | 6% | 3%
Tremor | 4% | <1% | 5% | 0%
Concentration Impaired | 3% | <1% | 1% | 0%
Nervousness | 2% | <1% | 3% | 2%
Anxiety | 2% | 1% | - | -
Lack of Emotion | 2% | <1% | - | -
Depression | - | - | 2% | <1%
Vertigo | - | - | 2% | <1%
Abnormal Dreams | 1% | <1% | - | -
Amnesia | - | - | 1% | 0%
Respiratory System
Sinusitis | - | - | 4% | 2%
Yawn | 2% | <1% | - | -
Bronchitis | - | - | 2% | 0%
Cough Increased | 1% | <1% | - | -
Skin and Appendages
Sweating | 7% | <1% | 6% | <1%
Special Senses
Abnormal Vision | - | - | 1% | 0%
Urogenital System
Female Genital Disordersd | 8% | 1% | 2% | 0%
Menorrhagia | 1% | <1% | - | -
Vaginal Moniliasis | 1% | <1% | - | -
Menstrual Disorder | - | - | 1% | 0%

a. Adverse events for which the reporting rate of PAXIL CR was less than or equal to the placebo rate are not included. These events for continuous dosing are: Abdominal pain, back pain, pain, trauma, weight gain, myalgia, pharyngitis, respiratory disorder, rhinitis, sinusitis, pruritis, dysmenorrhea, menstrual disorder, urinary tract infection, and vomiting. The events for luteal phase dosing are: Allergic reaction, back pain, headache, infection, pain, trauma, myalgia, anxiety, pharyngitis, respiratory disorder, cystitis, and dysmenorrhea.

b. <1% means greater than zero and less than 1%.

c. The luteal phase and continuous dosing PMDD trials were not designed for making direct comparisons between the 2 dosing regimens. Therefore, a comparison between the 2 dosing regimens of the PMDD trials of incidence rates shown in Table 6 should be avoided.

d. Mostly anorgasmia or difficulty achieving orgasm.

Dose Dependency of Adverse Events

Table 7 shows results in PMDD trials of common adverse events, defined as events with an incidence of ≥1% with 25 mg of PAXIL CR that was at least twice that with 12.5 mg of PAXIL CR and with placebo.

Table 7. Incidence of Common Adverse Events in Placebo, 12.5 mg, and 25 mg of PAXIL CR in a Pool of 3 Fixed-Dose PMDD Trials
 | PAXIL CR; 25 mg; (n = 348) | PAXIL CR; 12.5 mg; (n = 333) | Placebo; (n = 349)
Common Adverse Event
Sweating | 8.9% | 4.2% | 0.9%
Tremor | 6.0% | 1.5% | 0.3%
Concentration Impaired | 4.3% | 1.5% | 0.6%
Yawn | 3.2% | 0.9% | 0.3%
Paresthesia | 1.4% | 0.3% | 0.3%
Hyperkinesia | 1.1% | 0.3% | 0.0%
Vaginitis | 1.1% | 0.3% | 0.3%

A comparison of adverse event rates in a fixed-dose study comparing immediate-release paroxetine with placebo in the treatment of major depressive disorder revealed a clear dose dependency for some of the more common adverse events associated with the use of immediate-release paroxetine.

Male and Female Sexual Dysfunction With SSRIs

Although changes in sexual desire, sexual performance, and sexual satisfaction often occur as manifestations of a psychiatric disorder, they may also be a consequence of pharmacologic treatment. In particular, some evidence suggests that SSRIs can cause such untoward sexual experiences.

Reliable estimates of the incidence and severity of untoward experiences involving sexual desire, performance, and satisfaction are difficult to obtain; however, in part because patients and physicians may be reluctant to discuss them. Accordingly, estimates of the incidence of untoward sexual experience and performance cited in product labeling, are likely to underestimate their actual incidence.

The percentage of patients reporting symptoms of sexual dysfunction in the pool of 2 placebo-controlled trials in nonelderly patients with major depressive disorder, in the pool of 3 placebo-controlled trials in patients with panic disorder, in the placebo-controlled trial in patients with social anxiety disorder, and in the intermittent dosing and the pool of 3 placebo-controlled continuous dosing trials in female patients with PMDD are as follows:

 | Major Depressive Disorder |  | Panic Disorder |  | Social Anxiety Disorder |  | PMDD; Continuous Dosing |  | PMDD; Luteal Phase Dosing
 | PAXIL CR | Placebo | PAXIL CR | Placebo | PAXIL CR | Placebo | PAXIL CR | Placebo | PAXIL CR | Placebo
n (males) | 78 | 78 | 162 | 194 | 88 | 97 | n/a | n/a | n/a | n/a
Decreased Libido | 10% | 5% | 9% | 6% | 13% | 1% | n/a | n/a | n/a | n/a
Ejaculatory Disturbance | 26% | 1% | 27% | 3% | 15% | 1% | n/a | n/a | n/a | n/a
Impotence | 5% | 3% | 10% | 1% | 9% | 0% | n/a | n/a | n/a | n/a
n (females) | 134 | 133 | 282 | 251 | 98 | 87 | 681 | 349 | 246 | 120
Decreased Libido | 4% | 2% | 8% | 2% | 4% | 1% | 12% | 5% | 9% | 6%
Orgasmic Disturbance | 10% | <1% | 7% | 1% | 3% | 0% | 8% | 1% | 2% | 0%

There are no adequate, controlled studies examining sexual dysfunction with paroxetine treatment.

Paroxetine treatment has been associated with several cases of priapism. In those cases with a known outcome, patients recovered without sequelae.

While it is difficult to know the precise risk of sexual dysfunction associated with the use of SSRIs, physicians should routinely inquire about such possible side effects.

Weight and Vital Sign Changes

Significant weight loss may be an undesirable result of treatment with paroxetine for some patients but, on average, patients in controlled trials with PAXIL CR or the immediate-release formulation, had minimal weight loss (about 1 pound). No significant changes in vital signs (systolic and diastolic blood pressure, pulse, and temperature) were observed in patients treated with PAXIL CR, or immediate-release paroxetine hydrochloride, in controlled clinical trials.

ECG Changes

In an analysis of ECGs obtained in 682 patients treated with immediate-release paroxetine and 415 patients treated with placebo in controlled clinical trials, no clinically significant changes were seen in the ECGs of either group.

Liver Function Tests

In a pool of 2 placebo-controlled clinical trials, patients treated with PAXIL CR or placebo exhibited abnormal values on liver function tests at comparable rates. In particular, the controlled-release paroxetine-versus-placebo comparisons for alkaline phosphatase, SGOT, SGPT, and bilirubin revealed no differences in the percentage of patients with marked abnormalities.

In a study of elderly patients with major depressive disorder, 3 of 104 patients treated with PAXIL CR and none of 109 placebo patients experienced liver transaminase elevations of potential clinical concern.

Two of the patients treated with PAXIL CR dropped out of the study due to abnormal liver function tests; the third patient experienced normalization of transaminase levels with continued treatment. Also, in the pool of 3 studies of patients with panic disorder, 4 of 444 patients treated with PAXIL CR and none of 445 placebo patients experienced liver transaminase elevations of potential clinical concern. Elevations in all 4 patients decreased substantially after discontinuation of PAXIL CR. The clinical significance of these findings is unknown.

In placebo-controlled clinical trials with the immediate-release formulation of paroxetine, patients exhibited abnormal values on liver function tests at no greater rate than that seen in placebo-treated patients.

Hallucinations

In pooled clinical trials of immediate-release paroxetine hydrochloride, hallucinations were observed in 22 of 9,089 patients receiving drug and in 4 of 3,187 patients receiving placebo.

Other Events Observed During the Clinical Development of Paroxetine

The following adverse events were reported during the clinical development of PAXIL CR and/or the clinical development of the immediate-release formulation of paroxetine.

Adverse events for which frequencies are provided below occurred in clinical trials with the controlled-release formulation of paroxetine. During its premarketing assessment in major depressive disorder, panic disorder, social anxiety disorder, and PMDD, multiple doses of PAXIL CR were administered to 1,627 patients in phase 3 double-blind, controlled, outpatient studies. Untoward events associated with this exposure were recorded by clinical investigators using terminology of their own choosing. Consequently, it is not possible to provide a meaningful estimate of the proportion of individuals experiencing adverse events without first grouping similar types of untoward events into a smaller number of standardized event categories.

In the tabulations that follow, reported adverse events were classified using a COSTART-based dictionary. The frequencies presented, therefore, represent the proportion of the 1,627 patients exposed to PAXIL CR who experienced an event of the type cited on at least 1 occasion while receiving PAXIL CR. All reported events are included except those already listed in Tables 2 through 7 and those events where a drug cause was remote. If the COSTART term for an event was so general as to be uninformative, it was deleted or, when possible, replaced with a more informative term. It is important to emphasize that although the events reported occurred during treatment with paroxetine, they were not necessarily caused by it.

Events are further categorized by body system and listed in order of decreasing frequency according to the following definitions: Frequent adverse events are those occurring on 1 or more occasions in at least 1/100 patients (only those not already listed in the tabulated results from placebo-controlled trials appear in this listing); infrequent adverse events are those occurring in 1/100 to 1/1,000 patients; rare events are those occurring in fewer than 1/1,000 patients.

Adverse events for which frequencies are not provided occurred during the premarketing assessment of immediate-release paroxetine in phase 2 and 3 studies of major depressive disorder, obsessive compulsive disorder, panic disorder, social anxiety disorder, generalized anxiety disorder, and posttraumatic stress disorder. The conditions and duration of exposure to immediate-release paroxetine varied greatly and included (in overlapping categories) open and double-blind studies, uncontrolled and controlled studies, inpatient and outpatient studies, and fixed-dose and titration studies. Only those events not previously listed for controlled-release paroxetine are included. The extent to which these events may be associated with PAXIL CR is unknown.

Events are listed alphabetically within the respective body system. Events of major clinical importance are also described in the PRECAUTIONS section.

Body as a Whole

Infrequent were chills, face edema, fever, flu syndrome, malaise; rare were abscess, anaphylactoid reaction, anticholinergic syndrome, hypothermia; also observed were adrenergic syndrome, neck rigidity, sepsis.

Cardiovascular System

Infrequent were angina pectoris, bradycardia, hematoma, hypertension, hypotension, palpitation, postural hypotension, supraventricular tachycardia, syncope; rare were bundle branch block; also observed were arrhythmia nodal, atrial fibrillation, cerebrovascular accident, congestive heart failure, low cardiac output, myocardial infarct, myocardial ischemia, pallor, phlebitis, pulmonary embolus, supraventricular extrasystoles, thrombophlebitis, thrombosis, vascular headache, ventricular extrasystoles.

Digestive System

Infrequent were bruxism, dysphagia, eructation, gastritis, gastroenteritis, gastroesophageal reflux, gingivitis, hemorrhoids, liver function test abnormal, melena, pancreatitis, rectal hemorrhage, toothache, ulcerative stomatitis; rare were colitis, glossitis, gum hyperplasia, hepatosplenomegaly, increased salivation, intestinal obstruction, peptic ulcer, stomach ulcer, throat tightness; also observed were aphthous stomatitis, bloody diarrhea, bulimia, cardiospasm, cholelithiasis, duodenitis, enteritis, esophagitis, fecal impactions, fecal incontinence, gum hemorrhage, hematemesis, hepatitis, ileitis, ileus, jaundice, mouth ulceration, salivary gland enlargement, sialadenitis, stomatitis, tongue discoloration, tongue edema.

Endocrine System

Infrequent were ovarian cyst, testes pain; rare were diabetes mellitus, hyperthyroidism; also observed were goiter, hypothyroidism, thyroiditis.

Hemic and Lymphatic System

Infrequent were anemia, eosinophilia, hypochromic anemia, leukocytosis, leukopenia, lymphadenopathy, purpura; rare were thrombocytopenia; also observed were anisocytosis, basophilia, bleeding time increased, lymphedema, lymphocytosis, lymphopenia, microcytic anemia, monocytosis, normocytic anemia, thrombocythemia.

Metabolic and Nutritional Disorders

Infrequent were generalized edema, hyperglycemia, hypokalemia, peripheral edema, SGOT increased, SGPT increased, thirst; rare were bilirubinemia, dehydration, hyperkalemia, obesity; also observed were alkaline phosphatase increased, BUN increased, creatinine phosphokinase increased, gamma globulins increased, gout, hypercalcemia, hypercholesteremia, hyperphosphatemia, hypocalcemia, hypoglycemia, hyponatremia, ketosis, lactic dehydrogenase increased, non-protein nitrogen (NPN) increased.

Musculoskeletal System

Infrequent were arthritis, bursitis, tendonitis; rare were myasthenia, myopathy, myositis; also observed were generalized spasm, osteoporosis, tenosynovitis, tetany.

Nervous System

Frequent were depression; infrequent were amnesia, convulsion, depersonalization, dystonia, emotional lability, hallucinations, hyperkinesia, hypesthesia, hypokinesia, incoordination, libido increased, neuralgia, neuropathy, nystagmus, paralysis, vertigo; rare were ataxia, coma, diplopia, dyskinesia, hostility, paranoid reaction, torticollis, withdrawal syndrome; also observed were abnormal gait, akathisia, akinesia, aphasia, choreoathetosis, circumoral paresthesia, delirium, delusions, dysarthria, euphoria, extrapyramidal syndrome, fasciculations, grand mal convulsion, hyperalgesia, irritability, manic reaction, manic-depressive reaction, meningitis, myelitis, peripheral neuritis, psychosis, psychotic depression, reflexes decreased, reflexes increased, stupor, trismus.

Respiratory System

Frequent were pharyngitis; infrequent were asthma, dyspnea, epistaxis, laryngitis, pneumonia; rare were stridor; also observed were dysphonia, emphysema, hemoptysis, hiccups, hyperventilation, lung fibrosis, pulmonary edema, respiratory flu, sputum increased.

Skin and Appendages

Frequent were rash; infrequent were acne, alopecia, dry skin, eczema, pruritus, urticaria; rare were exfoliative dermatitis, furunculosis, pustular rash, seborrhea; also observed were angioedema, ecchymosis, erythema multiforme, erythema nodosum, hirsutism, maculopapular rash, skin discoloration, skin hypertrophy, skin ulcer, sweating decreased, vesiculobullous rash.

Special Senses

Infrequent were conjunctivitis, earache, keratoconjunctivitis, mydriasis, photophobia, retinal hemorrhage, tinnitus; rare were blepharitis, visual field defect; also observed were amblyopia, anisocoria, blurred vision, cataract, conjunctival edema, corneal ulcer, deafness, exophthalmos, glaucoma, hyperacusis, night blindness, parosmia, ptosis, taste loss.

Urogenital System

Frequent were dysmenorrhea*; infrequent were albuminuria, amenorrhea*, breast pain*, cystitis, dysuria, prostatitis*, urinary retention; rare were breast enlargement*, breast neoplasm*, female lactation, hematuria, kidney calculus, metrorrhagia*, nephritis, nocturia, pregnancy and puerperal disorders*, salpingitis, urinary incontinence, uterine fibroids enlarged*; also observed were breast atrophy, ejaculatory disturbance, endometrial disorder, epididymitis, fibrocystic breast, leukorrhea, mastitis, oliguria, polyuria, pyuria, urethritis, urinary casts, urinary urgency, urolith, uterine spasm, vaginal hemorrhage.

* Based on the number of men and women as appropriate.

Postmarketing Reports

Voluntary reports of adverse events in patients taking immediate-release paroxetine hydrochloride that have been received since market introduction and not listed above that may have no causal relationship with the drug include acute pancreatitis, elevated liver function tests (the most severe cases were deaths due to liver necrosis, and grossly elevated transaminases associated with severe liver dysfunction), Guillain-Barré syndrome, Stevens-Johnson syndrome, toxic epidermal necrolysis, priapism, syndrome of inappropriate ADH secretion, symptoms suggestive of prolactinemia and galactorrhea; extrapyramidal symptoms which have included akathisia, bradykinesia, cogwheel rigidity, dystonia, hypertonia, oculogyric crisis which has been associated with concomitant use of pimozide; tremor and trismus; status epilepticus, acute renal failure, pulmonary hypertension, allergic alveolitis, anaphylaxis, eclampsia, laryngismus, optic neuritis, porphyria, restless legs syndrome (RLS), ventricular fibrillation, ventricular tachycardia (including torsade de pointes), thrombocytopenia, hemolytic anemia, events related to impaired hematopoiesis (including aplastic anemia, pancytopenia, bone marrow aplasia, and agranulocytosis), and vasculitic syndromes (such as Henoch-Schönlein purpura). There has been a case report of an elevated phenytoin level after 4 weeks of immediate-release paroxetine and phenytoin coadministration. There has been a case report of severe hypotension when immediate-release paroxetine was added to chronic metoprolol treatment.

DRUG ABUSE AND DEPENDENCE

Controlled Substance Class

PAXIL CR is not a controlled substance.

Physical and Psychologic Dependence

PAXIL CR has not been systematically studied in animals or humans for its potential for abuse, tolerance or physical dependence. While the clinical trials did not reveal any tendency for any drug-seeking behavior, these observations were not systematic and it is not possible to predict on the basis of this limited experience the extent to which a CNS-active drug will be misused, diverted, and/or abused once marketed. Consequently, patients should be evaluated carefully for history of drug abuse, and such patients should be observed closely for signs of misuse or abuse of PAXIL CR (e.g., development of tolerance, incrementations of dose, drug-seeking behavior).

OVERDOSAGE

Human Experience

Since the introduction of immediate-release paroxetine hydrochloride in the United States, 342 spontaneous cases of deliberate or accidental overdosage during paroxetine treatment have been reported worldwide (circa 1999). These include overdoses with paroxetine alone and in combination with other substances. Of these, 48 cases were fatal and of the fatalities, 17 appeared to involve paroxetine alone. Eight fatal cases that documented the amount of paroxetine ingested were generally confounded by the ingestion of other drugs or alcohol or the presence of significant comorbid conditions. Of 145 non-fatal cases with known outcome, most recovered without sequelae. The largest known ingestion involved 2,000 mg of paroxetine (33 times the maximum recommended daily dose) in a patient who recovered.

Commonly reported adverse events associated with paroxetine overdosage include somnolence, coma, nausea, tremor, tachycardia, confusion, vomiting, and dizziness. Other notable signs and symptoms observed with overdoses involving paroxetine (alone or with other substances) include mydriasis, convulsions (including status epilepticus), ventricular dysrhythmias (including torsade de pointes), hypertension, aggressive reactions, syncope, hypotension, stupor, bradycardia, dystonia, rhabdomyolysis, symptoms of hepatic dysfunction (including hepatic failure, hepatic necrosis, jaundice, hepatitis, and hepatic steatosis), serotonin syndrome, manic reactions, myoclonus, acute renal failure, and urinary retention.

Overdosage Management

No specific antidotes for paroxetine are known. Treatment should consist of those general measures employed in the management of overdosage with any drugs effective in the treatment of major depressive disorder.

Ensure an adequate airway, oxygenation, and ventilation. Monitor cardiac rhythm and vital signs. General supportive and symptomatic measures are also recommended. Induction of emesis is not recommended. Due to the large volume of distribuiton of this drug, forced diuresis, dialysis, hemoperfusion, or exchange perfusion are unlikely to be of benefit.

A specific caution involves patients taking or recently having taken paroxetine who might ingest excessive quantities of a tricyclic antidepressant. In such a case, accumulation of the parent tricyclic and an active metabolite may increase the possibility of clinically significant sequelae and extend the time needed for close medical observation (see PRECAUTIONS: Drugs Metabolized by Cytochrome CYP2D6).

In managing overdosage, consider the possibility of multiple-drug involvement. The physician should consider contacting a poison control center for additional information on the treatment of any overdose. Telephone numbers for certified poison control centers are listed in the Physicians' Desk Reference (PDR).

DOSAGE AND ADMINISTRATION

Major Depressive Disorder

Usual Initial Dosage

PAXIL CR should be administered as a single daily dose, usually in the morning, with or without food. The recommended initial dose is 25 mg/day. Patients were dosed in a range of 25 mg to 62.5 mg/day in the clinical trials demonstrating the effectiveness of PAXIL CR in the treatment of major depressive disorder. As with all drugs effective in the treatment of major depressive disorder, the full effect may be delayed. Some patients not responding to a 25-mg dose may benefit from dose increases, in 12.5-mg/day increments, up to a maximum of 62.5 mg/day. Dose changes should occur at intervals of at least 1 week.

Patients should be cautioned that PAXIL CR should not be chewed or crushed, and should be swallowed whole.

Maintenance Therapy

There is no body of evidence available to answer the question of how long the patient treated with PAXIL CR should remain on it. It is generally agreed that acute episodes of major depressive disorder require several months or longer of sustained pharmacologic therapy. Whether the dose of an antidepressant needed to induce remission is identical to the dose needed to maintain and/or sustain euthymia is unknown.

Systematic evaluation of the efficacy of immediate-release paroxetine hydrochloride has shown that efficacy is maintained for periods of up to 1 year with doses that averaged about 30 mg, which corresponds to a 37.5-mg dose of PAXIL CR, based on relative bioavailability considerations (see CLINICAL PHARMACOLOGY: Pharmacokinetics).

Panic Disorder

Usual Initial Dosage

PAXIL CR should be administered as a single daily dose, usually in the morning. Patients should be started on 12.5 mg/day. Dose changes should occur in 12.5-mg/day increments and at intervals of at least 1 week. Patients were dosed in a range of 12.5 to 75 mg/day in the clinical trials demonstrating the effectiveness of PAXIL CR. The maximum dosage should not exceed 75 mg/day.

Patients should be cautioned that PAXIL CR should not be chewed or crushed, and should be swallowed whole.

Maintenance Therapy

Long-term maintenance of efficacy with the immediate-release formulation of paroxetine was demonstrated in a 3-month relapse prevention trial. In this trial, patients with panic disorder assigned to immediate-release paroxetine demonstrated a lower relapse rate compared to patients on placebo. Panic disorder is a chronic condition, and it is reasonable to consider continuation for a responding patient. Dosage adjustments should be made to maintain the patient on the lowest effective dosage, and patients should be periodically reassessed to determine the need for continued treatment.

Social Anxiety Disorder

Usual Initial Dosage

PAXIL CR should be administered as a single daily dose, usually in the morning, with or without food. The recommended initial dose is 12.5 mg/day. Patients were dosed in a range of 12.5 mg to 37.5 mg/day in the clinical trial demonstrating the effectiveness of PAXIL CR in the treatment of social anxiety disorder. If the dose is increased, this should occur at intervals of at least 1 week, in increments of 12.5 mg/day, up to a maximum of 37.5 mg/day.

Patients should be cautioned that PAXIL CR should not be chewed or crushed, and should be swallowed whole.

Maintenance Therapy

There is no body of evidence available to answer the question of how long the patient treated with PAXIL CR should remain on it. Although the efficacy of PAXIL CR beyond 12 weeks of dosing has not been demonstrated in controlled clinical trials, social anxiety disorder is recognized as a chronic condition, and it is reasonable to consider continuation of treatment for a responding patient. Dosage adjustments should be made to maintain the patient on the lowest effective dosage, and patients should be periodically reassessed to determine the need for continued treatment.

Premenstrual Dysphoric Disorder

Usual Initial Dosage

PAXIL CR should be administered as a single daily dose, usually in the morning, with or without food. PAXIL CR may be administered either daily throughout the menstrual cycle or limited to the luteal phase of the menstrual cycle, depending on physician assessment. The recommended initial dose is 12.5 mg/day. In clinical trials, both 12.5 mg/day and 25 mg/day were shown to be effective. Dose changes should occur at intervals of at least 1 week.

Patients should be cautioned that PAXIL CR should not be chewed or crushed, and should be swallowed whole.

Maintenance/Continuation Therapy

The effectiveness of PAXIL CR for a period exceeding 3 menstrual cycles has not been systematically evaluated in controlled trials. However, women commonly report that symptoms worsen with age until relieved by the onset of menopause. Therefore, it is reasonable to consider continuation of a responding patient. Patients should be periodically reassessed to determine the need for continued treatment.

Special Populations

Treatment of Pregnant Women During the Third Trimester

Neonates exposed to PAXIL CR and other SSRIs or SNRIs, late in the third trimester have developed complications requiring prolonged hospitalization, respiratory support, and tube feeding (see WARNINGS: Usage in Pregnancy). When treating pregnant women with paroxetine during the third trimester, the physician should carefully consider the potential risks and benefits of treatment. The physician may consider tapering paroxetine in the third trimester.

Dosage for Elderly or Debilitated Patients, and Patients With Severe Renal or Hepatic Impairment

The recommended initial dose of PAXIL CR is 12.5 mg/day for elderly patients, debilitated patients, and/or patients with severe renal or hepatic impairment. Increases may be made if indicated. Dosage should not exceed 50 mg/day.

Switching Patients to or From a Monoamine Oxidase Inhibitor Antidepressant

At least 14 days should elapse between discontinuation of an MAOI intended to treat depression and initiation of therapy with PAXIL CR. Conversely, at least 14 days should be allowed after stopping PAXIL CR before starting an MAOI antidepressant (see CONTRAINDICATIONS).

Use of PAXIL CR With Reversible MAOIs Such as Linezolid or Methylene Blue

Do not start PAXIL CR in a patient who is being treated with linezolid or methylene blue because there is increased risk of serotonin syndrome or NMS-like reactions. In a patient who requires more urgent treatment of a psychiatric condition, non-pharmacological interventions, including hospitalization, should be considered (see CONTRAINDICATIONS). In some cases, a patient receiving therapy with PAXIL CR may require urgent treatment with linezolid or methylene blue. If acceptable alternatives to linezolid or methylene blue treatment are not available and the potential benefits of linezolid or methylene blue treatment are judged to outweigh the risks of serotonin syndrome or NMS-like reactions in a particular patient, PAXIL CR should be stopped promptly, and linezolid or methylene blue can be administered. The patient should be monitored for symptoms of serotonin syndrome or NMS-like reactions for 2 weeks or until 24 hours after the last dose of linezolid or methylene blue, whichever comes first. Therapy with PAXIL CR may be resumed 24 hours after the last dose of linezolid or methylene blue (see WARNINGS).

Discontinuation of Treatment With PAXIL CR

Symptoms associated with discontinuation of immediate-release paroxetine hydrochloride or PAXIL CR have been reported (see PRECAUTIONS: Discontinuation of Treatment with PAXIL CR). Patients should be monitored for these symptoms when discontinuing treatment, regardless of the indication for which PAXIL CR is being prescribed. A gradual reduction in the dose rather than abrupt cessation is recommended whenever possible. If intolerable symptoms occur following a decrease in the dose or upon discontinuation of treatment, then resuming the previously prescribed dose may be considered. Subsequently, the physician may continue decreasing the dose but at a more gradual rate.

HOW SUPPLIED

PAXIL CR is supplied as an enteric film-coated, controlled-release, round tablet, as follows:

12.5-mg yellow tablets

NDC 54868-5347-0 Bottles of 30 (engraved with PAXIL CR and 12.5)

25-mg pink tablets

NDC 54868-4791-0 Bottles of 30 (engraved with PAXIL CR and 25)

37.5 mg blue tablets

NDC 54868-5365-0 Bottles of 30 (engraved with PAXIL CR and 37.5)

Store at or below 25°C (77°F) [see USP].

PAXIL CR is a registered trademark of GlaxoSmithKline.

GEOMATRIX is a trademark of Jago Pharma, Muttenz, Switzerland.

GlaxoSmithKline

Research Triangle Park, NC 27709

©2011, GlaxoSmithKline. All rights reserved.

July 2011 PCR:40PI

Additional barcode labeling by:
Physicians Total Care, Inc.
Tulsa, OK 74146

Medication Guide

PAXIL CR® (PAX-il) (paroxetine hydrochloride) Controlled-Release Tablets

Read the Medication Guide that comes with PAXIL CR before you start taking it and each time you get a refill. There may be new information. This Medication Guide does not take the place of talking to your healthcare provider about your medical condition or treatment. Talk with your healthcare provider if there is something you do not understand or want to learn more about.

What is the most important information I should know about PAXIL CR?

PAXIL CR and other antidepressant medicines may cause serious side effects, including:

1. Suicidal thoughts or actions:

- PAXIL CR and other antidepressant medicines may increase suicidal thoughts or actions in some children, teenagers, and young adults within the first few months of treatment or when the dose is changed.
- Depression or other serious mental illnesses are the most important causes of suicidal thoughts or actions.
- Watch for these changes and call your healthcare provider right away if you notice:
  - New or sudden changes in mood, behavior, actions, thoughts, or feelings, especially if severe.
  - Pay particular attention to such changes when PAXIL CR is started or when the dose is changed.

Keep all follow-up visits with your healthcare provider and call between visits if you are worried about symptoms.

Call your healthcare provider right away if you have any of the following symptoms, or call 911 if an emergency, especially if they are new, worse, or worry you:

- attempts to commit suicide
- acting on dangerous impulses
- acting aggressive or violent
- thoughts about suicide or dying
- new or worse depression
- new or worse anxiety or panic attacks
- feeling agitated, restless, angry, or irritable
- trouble sleeping
- an increase in activity and talking more than what is normal for you
- other unusual changes in behavior or mood

Call your healthcare provider right away if you have any of the following symptoms, or call 911 if an emergency. PAXIL CR may be associated with these serious side effects:

2. Serotonin Syndrome or Neuroleptic Malignant Syndrome-like reactions. This condition can be life-threatening and may include:

- agitation, hallucinations, coma, or other changes in mental status
- coordination problems or muscle twitching (overactive reflexes)
- racing heartbeat, high or low blood pressure
- sweating or fever
- nausea, vomiting, or diarrhea
- muscle rigidity

3. Severe allergic reactions:

- trouble breathing
- swelling of the face, tongue, eyes, or mouth
- rash, itchy welts (hives), or blisters, alone or with fever or joint pain

4. Abnormal bleeding: PAXIL CR and other antidepressant medicines may increase your risk of bleeding or bruising, especially if you take the blood thinner warfarin (Coumadin®, Jantoven®), a non-steroidal anti-inflammatory drug (NSAIDs, like ibuprofen or naproxen), or aspirin.

5. Seizures or convulsions

6. Manic episodes:

- greatly increased energy
- severe trouble sleeping
- racing thoughts
- reckless behavior
- unusually grand ideas
- excessive happiness or irritability
- talking more or faster than usual

7. Changes in appetite or weight. Children and adolescents should have height and weight monitored during treatment.

8. Low salt (sodium) levels in the blood. Elderly people may be at greater risk for this. Symptoms may include:

- headache
- weakness or feeling unsteady
- confusion, problems concentrating or thinking, or memory problems

Do not stop PAXIL CR without first talking to your healthcare provider. Stopping PAXIL CR too quickly may cause serious symptoms including:

- anxiety, irritability, high or low mood, feeling restless, or changes in sleep habits
- headache, sweating, nausea, dizziness
- electric shock-like sensations, shaking, confusion

What is PAXIL CR?

PAXIL CR is a prescription medicine used to treat depression. It is important to talk with your healthcare provider about the risks of treating depression and also the risks of not treating it. You should discuss all treatment choices with your healthcare provider. PAXIL CR is also used to treat:

- Major Depressive Disorder (MDD)
- Panic Disorder
- Social Anxiety Disorder
- Premenstrual Dysphoric Disorder (PMDD)

Talk to your healthcare provider if you do not think that your condition is getting better with treatment using PAXIL CR.

Who should not take PAXIL CR?

Do not take PAXIL CR if you:

- are allergic to paroxetine or any of the ingredients in PAXIL CR. See the end of this Medication Guide for a complete list of ingredients in PAXIL CR.
- take a monoamine oxidase inhibitor (MAOI). Ask your healthcare provider or pharmacist if you are not sure if you take an MAOI, including the antibiotic linezolid.
- Do not take an MAOI within 2 weeks of stopping PAXIL CR unless directed to do so by your physician..
- Do not start PAXIL CR if you stopped taking an MAOI in the last 2 weeks unless directed to do so by your physician.
- People who take PAXIL CR close in time to an MAOI may have serious or even life-threatening side effects. Get medical help right away if you have any of these symptoms:
  - high fever
  - uncontrolled muscle spasms
  - stiff muscles
  - rapid changes in heart rate or blood pressure
  - confusion
  - loss of consciousness (pass out)

- take MELLARIL® (thioridazine). Do not take MELLARIL® together with PAXIL CR because this can cause serious heart rhythm problems or sudden death.
- take the antipsychotic medicine pimozide (ORAP®) because this can cause serious heart problems.

What should I tell my healthcare provider before taking PAXIL CR? Ask if you are not sure.

Before starting PAXIL CR, tell your healthcare provider if you:

- are pregnant, may be pregnant, or plan to become pregnant. There is a possibility that PAXIL CR may harm your unborn baby, including an increased risk of birth defects, particularly heart defects. Other risks may include a serious condition in which there is not enough oxygen in the baby’s blood. Your baby may also have certain other symptoms shortly after birth. Premature births have also been reported in some women who used PAXIL CR during pregnancy
- are breastfeeding. PAXIL CR passes into your milk. Talk to your healthcare provider about the best way to feed your baby while taking PAXIL CR.
- are taking certain drugs such as:
  - triptans used to treat migraine headache
  - other antidepressants (SSRIs, SNRIs, tricyclics, or lithium) or antipsychotics
  - drugs that affect serotonin, such as lithium, tramadol, tryptophan, St. John’s wort
  - certain drugs used to treat irregular heart beats
  - certain drugs used to treat schizophrenia
  - certain drugs used to treat HIV infection
  - certain drugs that affect the blood, such as warfarin, aspirin, and ibuprofen
  - certain drugs used to treat epilepsy
  - atomoxetine
  - cimetidine
  - fentanyl
  - metoprolol
  - pimozide
  - procyclidine
  - tamoxifen
- have liver problems
- have kidney problems
- have heart problems
- have or had seizures or convulsions
- have bipolar disorder or mania
- have low sodium levels in your blood
- have a history of a stroke
- have high blood pressure
- have or had bleeding problems
- have glaucoma (high pressure in the eye)

Tell your healthcare provider about all the medicines you take, including prescription and non-prescription medicines, vitamins, and herbal supplements. PAXIL CR and some medicines may interact with each other, may not work as well, or may cause serious side effects.

Your healthcare provider or pharmacist can tell you if it is safe to take PAXIL CR with your other medicines. Do not start or stop any medicine while taking PAXIL CR without talking to your healthcare provider first.

BOXED WARNING

If you take PAXIL CR, you should not take any other medicines that contain paroxetine, including PAXIL and PEXEVA® (paroxetine mesylate).

How should I take PAXIL CR?

- Take PAXIL CR exactly as prescribed. Your healthcare provider may need to change the dose of PAXIL CR until it is the right dose for you.
- PAXIL CR may be taken with or without food.
- PAXIL CR controlled-release tablets should not be chewed or crushed and should be swallowed whole.
- If you miss a dose of PAXIL CR, take the missed dose as soon as you remember. If it is almost time for the next dose, skip the missed dose and take your next dose at the regular time. Do not take two doses of PAXIL CR at the same time.
- If you take too much PAXIL CR, call your healthcare provider or poison control center right away, or get emergency treatment.
- Do not stop taking PAXIL CR suddenly without talking to your doctor (unless you have symptoms of a severe allergic reaction). If you need to stop taking PAXIL CR, your healthcare provider can tell you how to safely stop taking it.

What should I avoid while taking PAXIL CR?

PAXIL CR can cause sleepiness or may affect your ability to make decisions, think clearly, or react quickly. You should not drive, operate heavy machinery, or do other dangerous activities until you know how PAXIL CR affects you. Do not drink alcohol while using PAXIL CR.

What are possible side effects of PAXIL CR?

PAXIL CR may cause serious side effects, including all of those described in the section entitled “What is the most important information I should know about PAXIL CR?”

Common possible side effects in people who take PAXIL CR include:

- nausea
- sleepiness
- feeling anxious or trouble sleeping
- sexual problems
- sweating
- shaking
- constipation
- yawning
- blurred vision
- diarrhea
- dry mouth
- decreased appetite
- weakness

Tell your healthcare provider if you have any side effect that bothers you or that does not go away. These are not all the possible side effects of PAXIL CR. For more information, ask your healthcare provider or pharmacist.

CALL YOUR DOCTOR FOR MEDICAL ADVICE ABOUT SIDE EFFECTS. YOU MAY REPORT SIDE EFFECTS TO THE FDA AT 1-800-FDA-1088 or 1-800-332-1088.

How should I store PAXIL CR?

- Store PAXIL CR at or below room temperature (77ºF or 25ºC).
- Keep PAXIL CR away from light.
- Keep bottle of PAXIL CR closed tightly.

Keep PAXIL CR and all medicines out of the reach of children.

General information about PAXIL CR

Medicines are sometimes prescribed for purposes other than those listed in a Medication Guide. Do not use PAXIL CR for a condition for which it was not prescribed. Do not give PAXIL CR to other people, even if they have the same condition. It may harm them.

This Medication Guide summarizes the most important information about PAXIL CR. If you would like more information, talk with your healthcare provider. You may ask your healthcare provider or pharmacist for information about PAXIL CR that is written for healthcare professionals.

For more information about PAXIL CR call 1-888-825-5249 or go to www.us.gsk.com.

What are the ingredients in PAXIL CR?

Active ingredient: paroxetine hydrochloride

Inactive ingredients in tablets:hypromellose, polyvinylpyrrolidone, lactose monohydrate, magnesium stearate, silicon dioxide, glyceryl behenate, methacrylic acid copolymer type C, sodium lauryl sulfate, polysorbate 80, talc, triethyl citrate, titanium dioxide, polyethylene glycols, and 1 or more of the following colorants: Yellow ferric oxide, red ferric oxide, D&C Red No. 30 aluminum lake, FD&C Yellow No. 6 aluminum lake, D&C Yellow No. 10 aluminum lake, FD&C Blue No. 2 aluminum lake.

PAXIL and PAXIL CR are registered trademarks of GlaxoSmithKline. The other brands listed are trademarks of their respective owners and are not trademarks of GlaxoSmithKline. The makers of these brands are not affiliated with and do not endorse GlaxoSmithKline or its products.

This Medication Guide has been approved by the U.S. Food and Drug Administration.

GlaxoSmithKline

Research Triangle Park, NC 27709

©2011, GlaxoSmithKline. All rights reserved.

July 2011 PCR:5MG

PACKAGE LABEL

Principal Display Panel

12.5 mg

NDC 54868-5347-0

PAXIL CR®

PAROXETINE HCl

CONTROLLED-RELEASE TABLETS

30 Tablets

Rx only

Federal Law requires dispensing of Paxil CR® with the Medication Guide under this label.

Store at or below 25oC (77oF) [see USP].

Each controlled-release tablet contains paroxetine hydrochloride equivalent to 12.5 mg paroxetine.

Dosage: See accompanying prescribing information.

Important: Use safety closures when dispensing this product unless otherwise directed by physician or requested by purchaser.

PACKAGE LABEL

Principal Display Panel

25 mg

NDC 54868-4791-0

PAXIL CR®

PAROXETINE HCl

CONTROLLED-RELEASE TABLETS

30 Tablets

Rx only

Federal Law requires dispensing of Paxil CR® with the Medication Guide under this label.

Store at or below 25oC (77oF) [see USP].

Each controlled-release tablet contains paroxetine hydrochloride equivalent to 25 mg paroxetine.

Dosage: See accompanying prescribing information.

Important: Use safety closures when dispensing this product unless otherwise directed by physician or requested by purchaser.

PACKAGE LABEL

Principal Display Panel

37.5 mg

NDC 54868-5365-0

PAXIL CR®

PAROXETINE HCl

CONTROLLED-RELEASE TABLETS

30 Tablets

Rx only

Federal Law requires dispensing of Paxil CR® with the Medication Guide under this label.

Store at or below 25oC (77oF) [see USP].

Each controlled-release tablet contains paroxetine hydrochloride equivalent to 37.5 mg paroxetine.

Dosage: See accompanying prescribing information.

Important: Use safety closures when dispensing this product unless otherwise directed by physician or requested by purchaser.